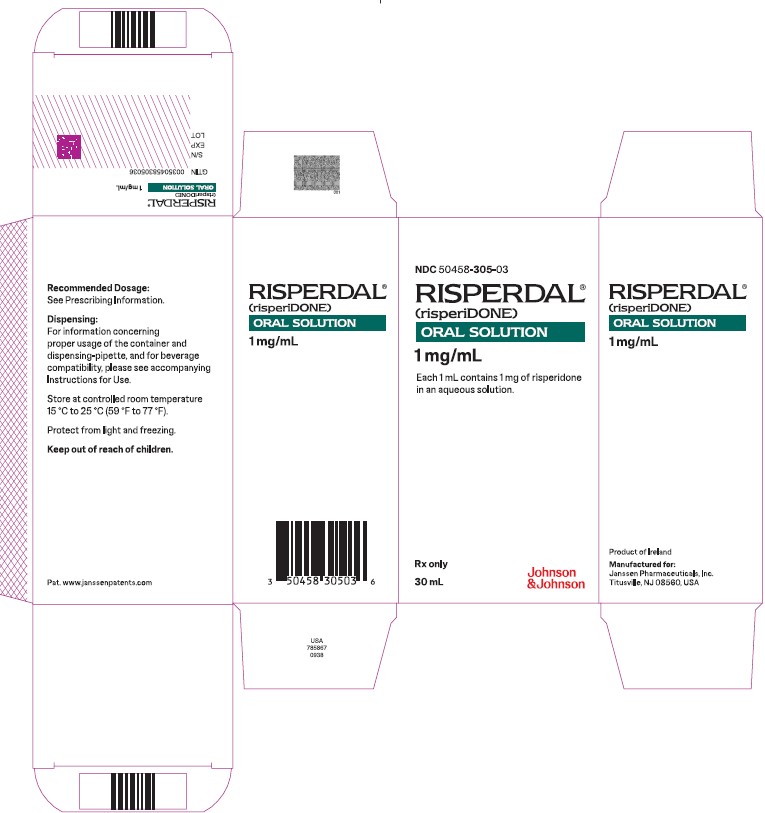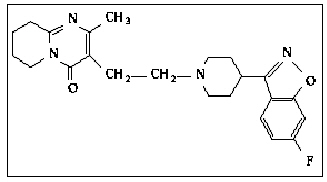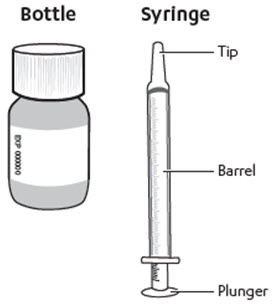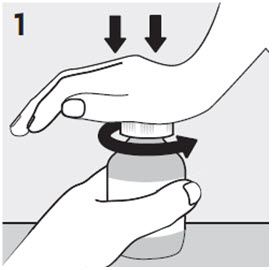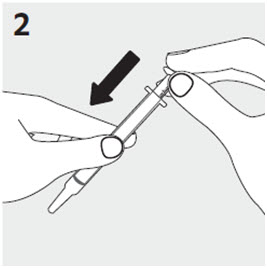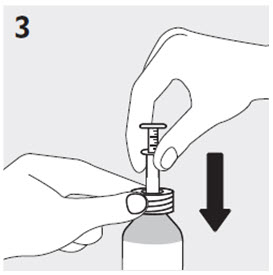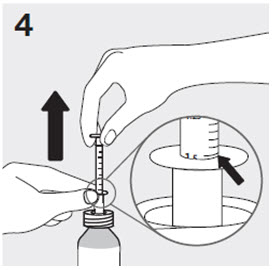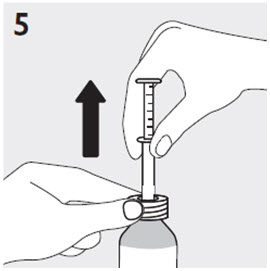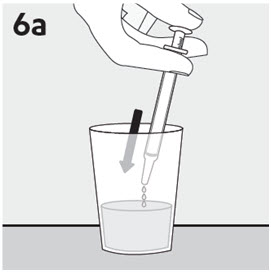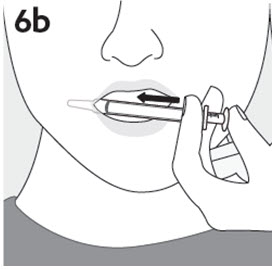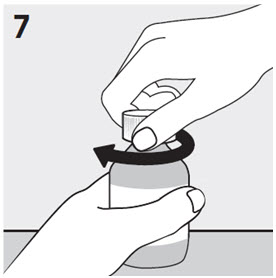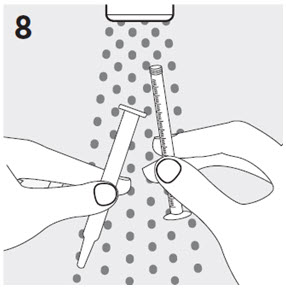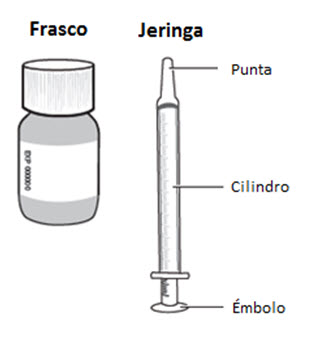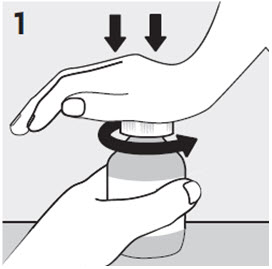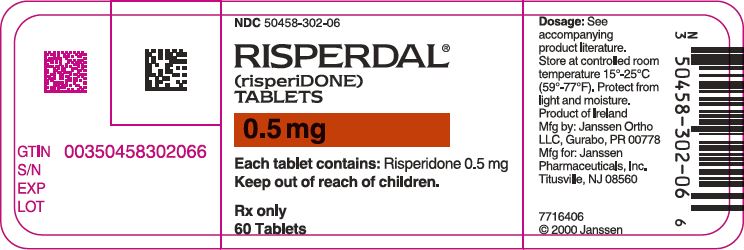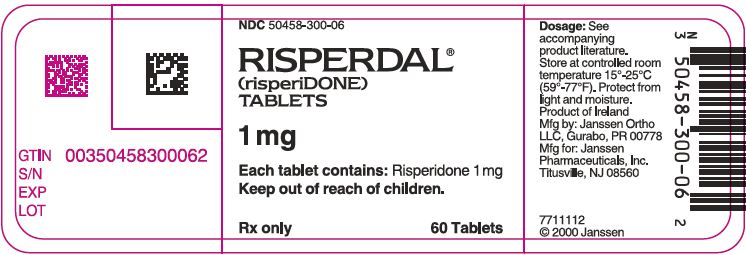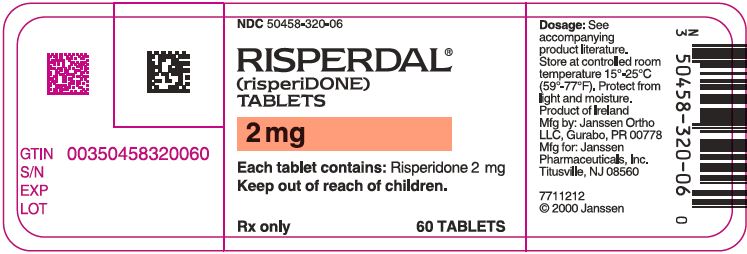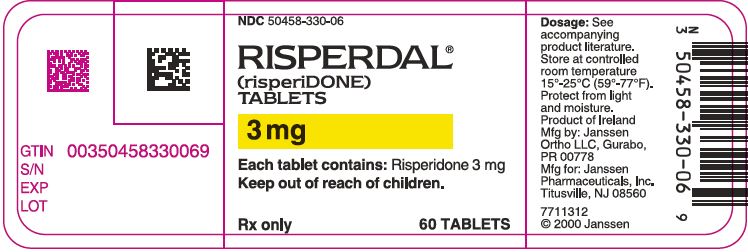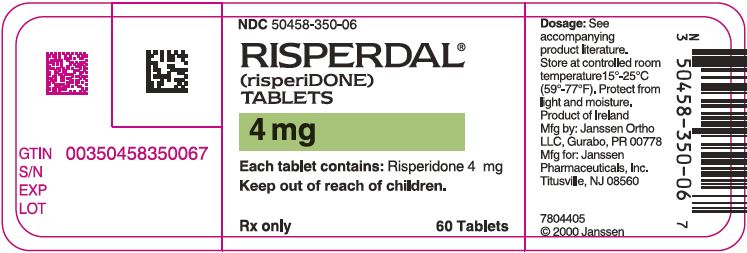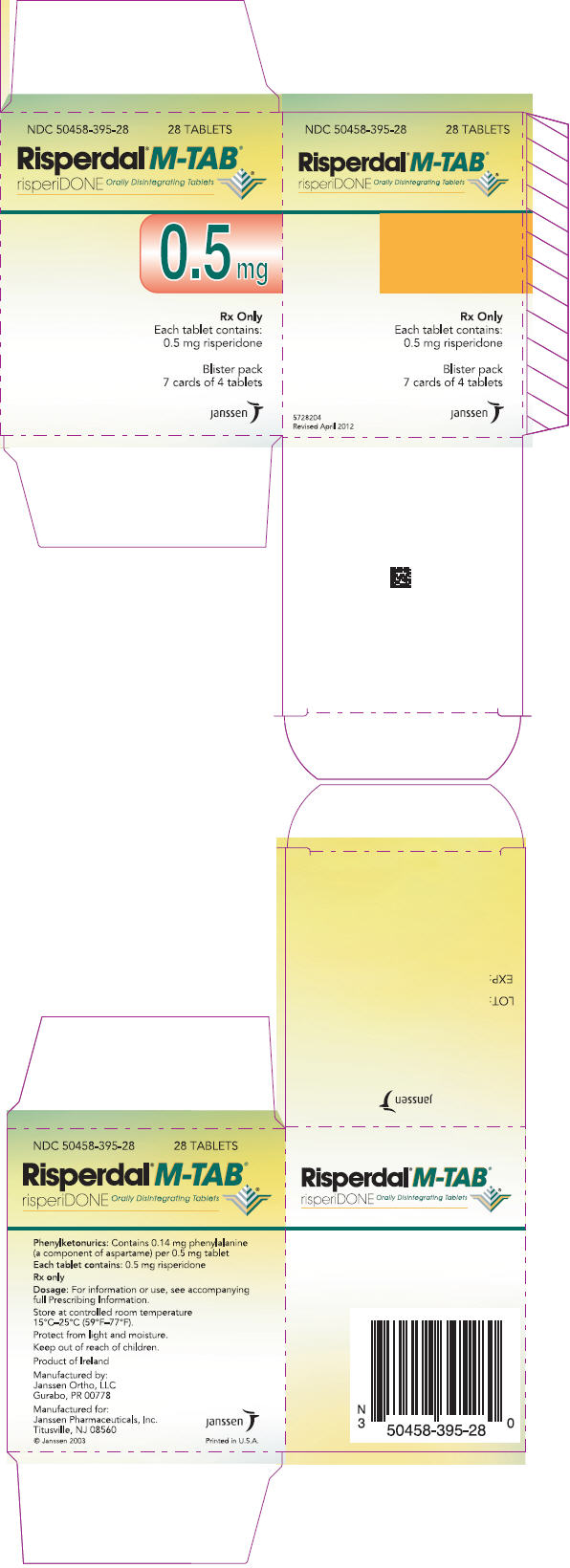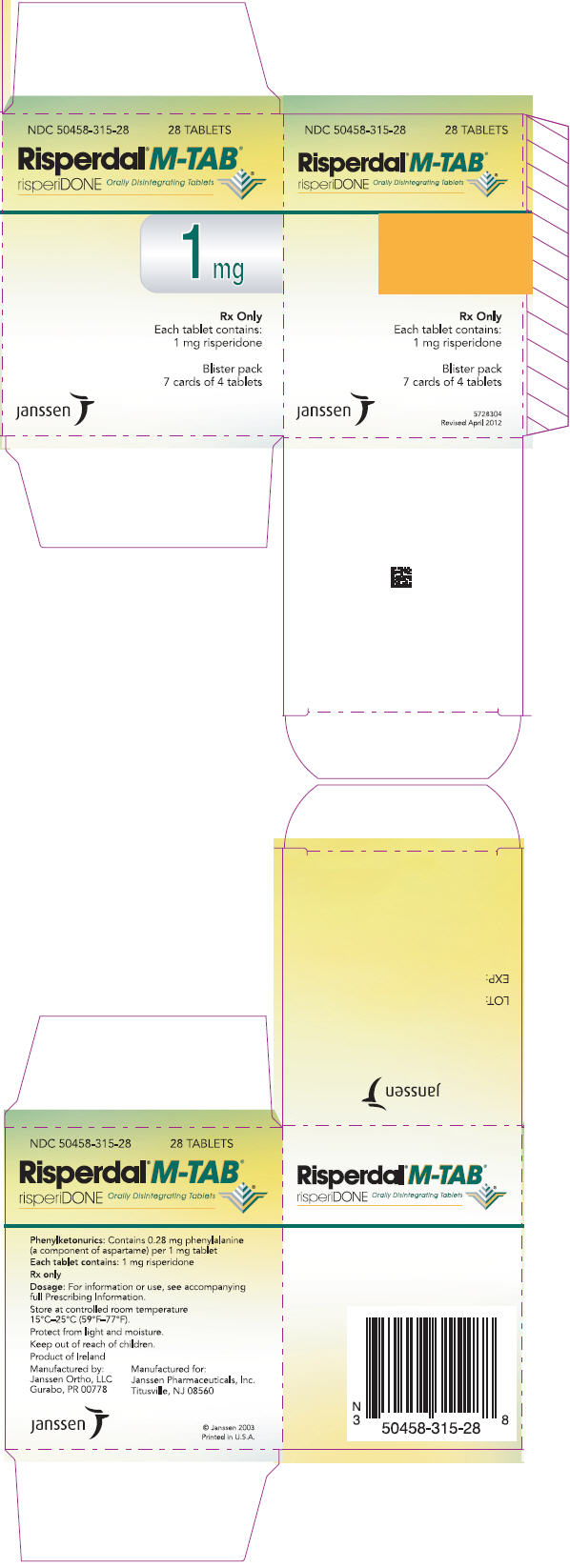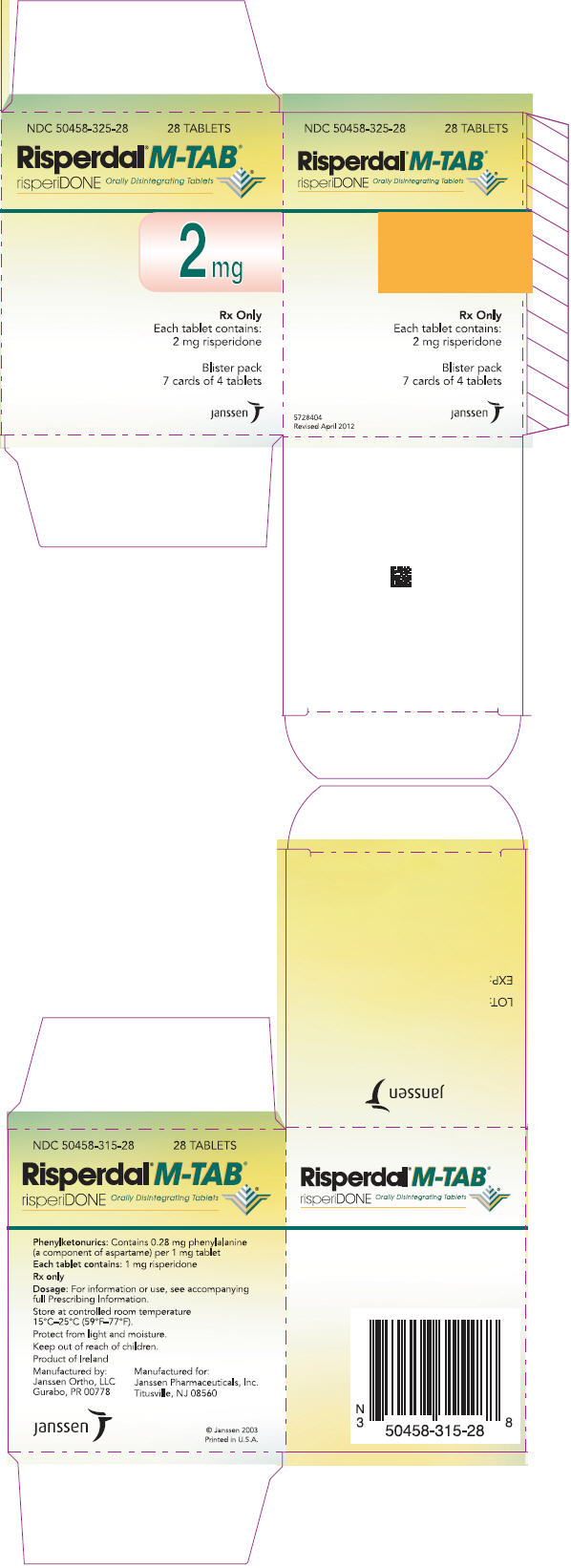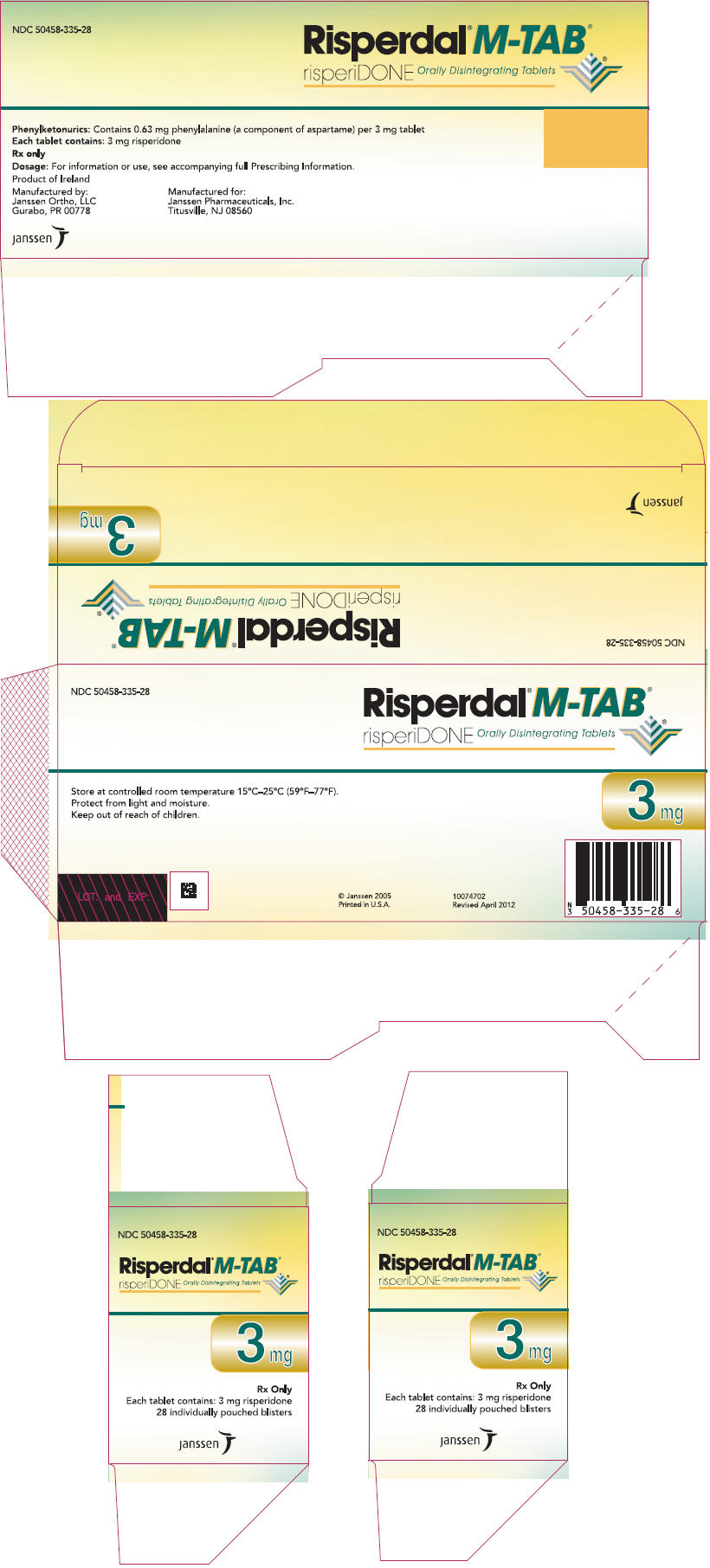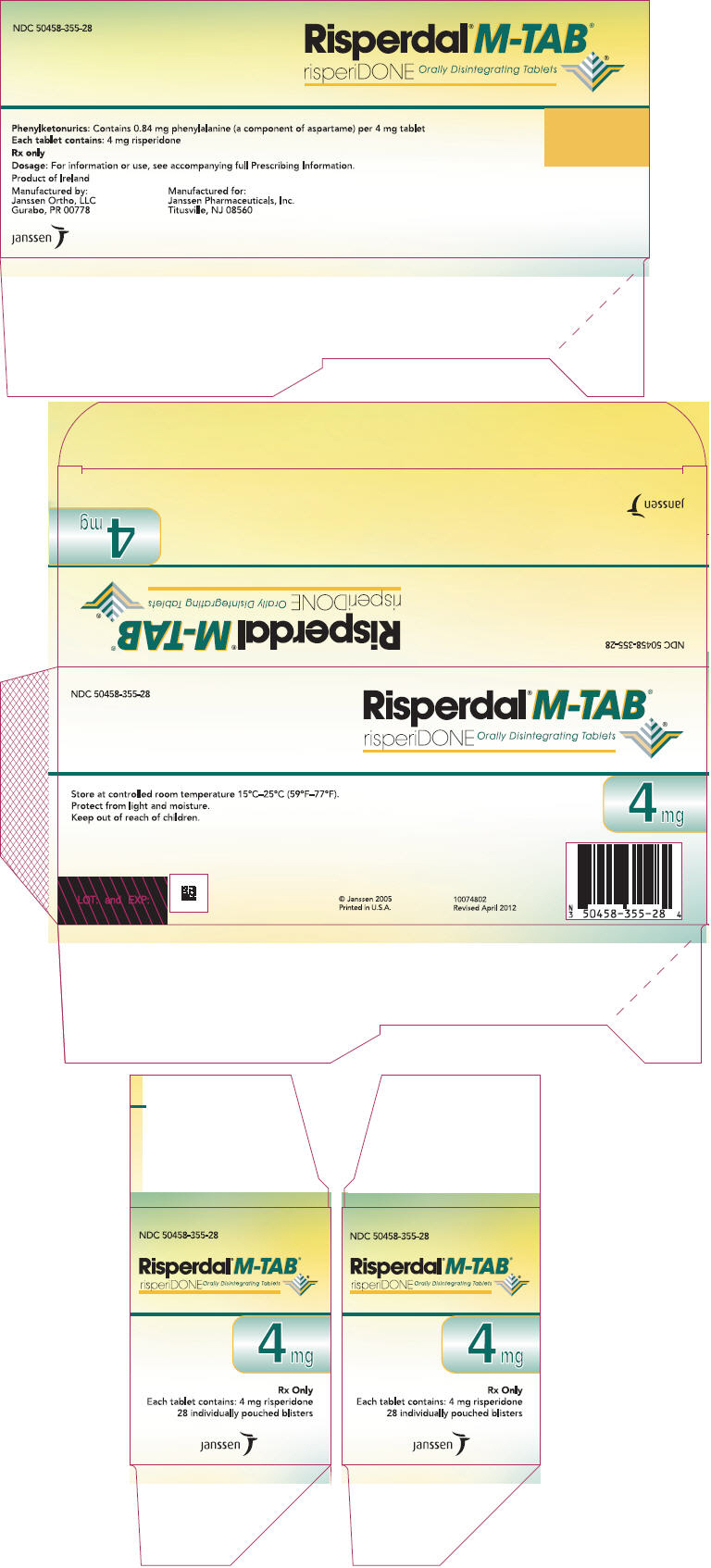 DRUG LABEL: RISPERDAL
NDC: 50458-302 | Form: TABLET
Manufacturer: Janssen Pharmaceuticals, Inc.
Category: prescription | Type: HUMAN PRESCRIPTION DRUG LABEL
Date: 20251111

ACTIVE INGREDIENTS: RISPERIDONE 0.5 mg/1 1
INACTIVE INGREDIENTS: SILICON DIOXIDE; HYPROMELLOSE, UNSPECIFIED; ANHYDROUS LACTOSE; MAGNESIUM STEARATE; MICROCRYSTALLINE CELLULOSE; PROPYLENE GLYCOL; SODIUM LAURYL SULFATE; STARCH, CORN; TALC; TITANIUM DIOXIDE; FERRIC OXIDE RED

HIGHLIGHTS OF PRESCRIBING INFORMATION

These highlights do not include all the information needed to use RISPERDAL®safely and effectively. See full prescribing information for RISPERDAL®.
RISPERDAL® (risperidone) tablets, for oral use
RISPERDAL® (risperidone) oral solution
RISPERDAL® M-TAB®(risperidone) orally disintegrating tablets
Initial U.S. Approval: 1993

WARNING: INCREASED MORTALITY IN ELDERLY PATIENTS WITH DEMENTIA-RELATED PSYCHOSIS

See full prescribing information for complete boxed warning.

Elderly patients with dementia-related psychosis treated with antipsychotic drugs are at an increased risk of death. RISPERDAL is not approved for use in patients with dementia-related psychosis. (5.1)

RECENT MAJOR CHANGES

Warnings and Precautions (5.6) | 1/2025

1 INDICATIONS AND USAGE

RISPERDAL is an atypical antipsychotic indicated for:

- Treatment of schizophrenia (1.1)
- As monotherapy or adjunctive therapy with lithium or valproate, for the treatment of acute manic or mixed episodes associated with Bipolar I Disorder (1.2)
- Treatment of irritability associated with autistic disorder (1.3)

2 DOSAGE AND ADMINISTRATION

- Recommended daily dosage:

 | Initial Dose | Target Dose | Effective Dose Range
Schizophrenia: adults (2.1) | 2 mg | 4 to 8 mg | 4 to 16 mg
Schizophrenia: adolescents (2.1) | 0.5 mg | 3 mg | 1 to 6 mg
Bipolar mania: adults (2.2) | 2 to 3 mg | 1 to 6 mg | 1 to 6 mg
Bipolar mania: in children and adolescents (2.2) | 0.5 mg | 1 to 2.5 mg | 1 to 6 mg
Irritability associated with autistic disorder (2.3) | 0.25 mg (Weight < 20 kg) 0.5 mg (Weight ≥20 kg) | 0.5 mg (<20 kg) 1 mg (≥20 kg) | 0.5 to 3 mg

- Severe Renal or Hepatic Impairment in Adults: Use a lower starting dose of 0.5 mg twice daily. May increase to dosages above 1.5 mg twice daily at intervals of at least one week. (2.4)
- Oral Solution: Can be administered directly from calibrated oral dosing syringe or mixed with beverage (water, coffee, orange juice, or low-fat milk). (2.6)
- M-TAB Orally Disintegrating Tablets: Open the blister only when ready to administer, and immediately place tablet on the tongue. Can be swallowed with or without liquid. (2.7)

3 DOSAGE FORMS AND STRENGTHS

- Tablets: 0.5 mg, 1 mg, 2 mg, 3 mg, and 4 mg (3)
- Oral solution: 1 mg per mL (3)
- Orally disintegrating tablets: 0.5 mg, 1 mg, 2 mg, 3 mg, and 4 mg (3)

4 CONTRAINDICATIONS

- Known hypersensitivity to risperidone, paliperidone, or to any excipients in RISPERDAL. (4)

5 WARNINGS AND PRECAUTIONS

- Cerebrovascular events, including stroke, in elderly patients with dementia-related psychosis: RISPERDAL is not approved for use in patients with dementia-related psychosis. (5.2)
- Neuroleptic Malignant Syndrome: Manage with immediate discontinuation of RISPERDAL and close monitoring. (5.3)
- Tardive dyskinesia: Consider discontinuing RISPERDAL if clinically indicated. (5.4)
- Metabolic Changes: Atypical antipsychotic drugs have been associated with metabolic changes that may increase cardiovascular/ cerebrovascular risk. These metabolic changes include hyperglycemia, dyslipidemia, and weight gain. (5.5)
  - Hyperglycemia and Diabetes Mellitus:Monitor patients for symptoms of hyperglycemia including polydipsia, polyuria, polyphagia, and weakness. Monitor glucose regularly in patients with diabetes or at risk for diabetes. (5.5)
  - Dyslipidemia:Undesirable alterations have been observed in patients treated with atypical antipsychotics. (5.5)
  - Weight Gain:Significant weight gain has been reported. Monitor weight gain. (5.5)
- Hyperprolactinemia: Prolactin elevations occur and persist during chronic administration. (5.6)
- Orthostatic hypotension: For patients at risk, consider a lower starting dose and slower titration. (5.7)
- Leukopenia, Neutropenia, and Agranulocytosis: Perform complete blood counts in patients with a history of clinically significant low white blood cell count (WBC). Consider discontinuing RISPERDAL if a clinically significant decline in WBC occurs in the absence of other causative factors. (5.9)
- Potential for cognitive and motor impairment: Use caution when operating machinery. (5.10)
- Seizures: Use cautiously in patients with a history of seizures or with conditions that lower the seizure threshold. (5.11)

6 ADVERSE REACTIONS

The most common adverse reactions in clinical trials (≥5% and twice placebo) were parkinsonism, akathisia, dystonia, tremor, sedation, dizziness, anxiety, blurred vision, nausea, vomiting, upper abdominal pain, stomach discomfort, dyspepsia, diarrhea, salivary hypersecretion, constipation, dry mouth, increased appetite, increased weight, fatigue, rash, nasal congestion, upper respiratory tract infection, nasopharyngitis, and pharyngolaryngeal pain. (6)

To report SUSPECTED ADVERSE REACTIONS, contact Janssen Pharmaceuticals, Inc. at 1-800-526-7736 or FDA at 1-800-FDA-1088 or www.fda.gov/medwatch

7 DRUG INTERACTIONS

- Carbamazepine and other enzyme inducers decrease plasma concentrations of risperidone. Increase the RISPERDAL dose up to double the patient's usual dose. Titrate slowly. (7.1)
- Fluoxetine, paroxetine, and other CYP 2D6 enzyme inhibitors increase plasma concentrations of risperidone. Reduce the initial dose. Do not exceed a final dose of 8 mg per day of RISPERDAL. (7.1)

8 USE IN SPECIFIC POPULATIONS

- Pregnancy: May cause extrapyramidal and/or withdrawal symptoms in neonates with third trimester exposure. (8.1)

FULL PRESCRIBING INFORMATION

WARNING: INCREASED MORTALITY IN ELDERLY PATIENTS WITH DEMENTIA-RELATED PSYCHOSIS

Elderly patients with dementia-related psychosis treated with antipsychotic drugs are at an increased risk of death. RISPERDAL is not approved for the treatment of patients with dementia-related psychosis. [see Warnings and Precautions (5.1)]

1 INDICATIONS AND USAGE

1.1 Schizophrenia

RISPERDAL (risperidone) is indicated for the treatment of schizophrenia. Efficacy was established in 4 short-term trials in adults, 2 short-term trials in adolescents (ages 13 to 17 years), and one long-term maintenance trial in adults [see Clinical Studies (14.1)] .

1.2 Bipolar Mania

Monotherapy

RISPERDAL is indicated for the treatment of acute manic or mixed episodes associated with Bipolar I Disorder. Efficacy was established in 2 short-term trials in adults and one short-term trial in children and adolescents (ages 10 to 17 years) [see Clinical Studies (14.2)] .

Adjunctive Therapy

RISPERDAL adjunctive therapy with lithium or valproate is indicated for the treatment of acute manic or mixed episodes associated with Bipolar I Disorder. Efficacy was established in one short-term trial in adults [see Clinical Studies (14.3)] .

1.3 Irritability Associated with Autistic Disorder

RISPERDAL is indicated for the treatment of irritability associated with autistic disorder, including symptoms of aggression towards others, deliberate self-injuriousness, temper tantrums, and quickly changing moods. Efficacy was established in 3 short-term trials in children and adolescents (ages 5 to 17 years) [see Clinical Studies (14.4)] .

2 DOSAGE AND ADMINISTRATION

Table 1. Recommended Daily Dosage by Indication
 | Initial Dose | Titration (Increments) | Target Dose | Effective Dose Range
Schizophrenia: adults (2.1) | 2 mg | 1 to 2 mg | 4 to 8 mg | 4 to 16 mg
Schizophrenia: adolescents (2.2) | 0.5 mg | 0.5 to 1 mg | 3 mg | 1 to 6 mg
Bipolar mania: adults (2.2) | 2 to 3 mg | 1 mg | 1 to 6 mg | 1 to 6 mg
Bipolar mania: children and adolescents (2.2) | 0.5 mg | 0.5 to 1 mg | 1 to 2.5 mg | 1 to 6 mg
Irritability in autistic disorder (2.3) | 0.25 mg Can increase to 0.5 mg by Day 4: (body weight less than 20 kg) 0.5 mg Can increase to 1 mg by Day 4: (body weight greater than or equal to 20 kg) | After Day 4, at intervals of > 2 weeks: 0.25 mg (body weight less than 20 kg) 0.5 mg (body weight greater than or equal to 20 kg) | 0.5 mg: (body weight less than 20 kg) 1 mg: (body weight greater than or equal to 20 kg) | 0.5 to 3 mg

Severe Renal and Hepatic Impairment in Adults: use a lower starting dose of 0.5 mg twice daily. May increase to dosages above 1.5 mg twice daily at intervals of one week or longer.

2.1 Schizophrenia

Adults

Usual Initial Dose

RISPERDAL can be administered once or twice daily. Initial dosing is 2 mg per day. May increase the dose at intervals of 24 hours or greater, in increments of 1 to 2 mg per day, as tolerated, to a recommended dose of 4 to 8 mg per day. In some patients, slower titration may be appropriate. Efficacy has been demonstrated in a range of 4 mg to 16 mg per day. However, doses above 6 mg per day for twice daily dosing were not demonstrated to be more efficacious than lower doses, were associated with more extrapyramidal symptoms and other adverse effects, and are generally not recommended. In a single study supporting once-daily dosing, the efficacy results were generally stronger for 8 mg than for 4 mg. The safety of doses above 16 mg per day has not been evaluated in clinical trials [see Clinical Studies (14.1)] .

Adolescents

The initial dose is 0.5 mg once daily, administered as a single-daily dose in the morning or evening. The dose may be adjusted at intervals of 24 hours or greater, in increments of 0.5 mg or 1 mg per day, as tolerated, to a recommended dose of 3 mg per day. Although efficacy has been demonstrated in studies of adolescent patients with schizophrenia at doses between 1 mg to 6 mg per day, no additional benefit was observed above 3 mg per day, and higher doses were associated with more adverse events. Doses higher than 6 mg per day have not been studied.

Patients experiencing persistent somnolence may benefit from administering half the daily dose twice daily.

Maintenance Therapy

While it is unknown how long a patient with schizophrenia should remain on RISPERDAL, the effectiveness of RISPERDAL 2 mg per day to 8 mg per day at delaying relapse was demonstrated in a controlled trial in adult patients who had been clinically stable for at least 4 weeks and were then followed for a period of 1 to 2 years [see Clinical Studies (14.1)] . Both adult and adolescent patients who respond acutely should generally be maintained on their effective dose beyond the acute episode. Patients should be periodically reassessed to determine the need for maintenance treatment.

Reinitiation of Treatment in Patients Previously Discontinued

Although there are no data to specifically address reinitiation of treatment, it is recommended that after an interval off RISPERDAL, the initial titration schedule should be followed.

Switching From Other Antipsychotics

There are no systematically collected data to specifically address switching schizophrenic patients from other antipsychotics to RISPERDAL, or treating patients with concomitant antipsychotics.

2.2 Bipolar Mania

Usual Dose

Adults

The initial dose range is 2 mg to 3 mg per day. The dose may be adjusted at intervals of 24 hours or greater, in increments of 1 mg per day. The effective dose range is 1 mg to 6 mg per day, as studied in the short-term, placebo-controlled trials. In these trials, short-term (3 week) anti-manic efficacy was demonstrated in a flexible dosage range of 1 mg to 6 mg per day [see Clinical Studies (14.2, 14.3)] . RISPERDAL doses higher than 6 mg per day were not studied.

Pediatrics

The initial dose is 0.5 mg once daily, administered as a single-daily dose in the morning or evening. The dose may be adjusted at intervals of 24 hours or greater, in increments of 0.5 mg or 1 mg per day, as tolerated, to the recommended target dose of 1 mg to 2.5 mg per day. Although efficacy has been demonstrated in studies of pediatric patients with bipolar mania at doses between 0.5 mg and 6 mg per day, no additional benefit was observed above 2.5 mg per day, and higher doses were associated with more adverse events. Doses higher than 6 mg per day have not been studied.

Patients experiencing persistent somnolence may benefit from administering half the daily dose twice daily.

Maintenance Therapy

There is no body of evidence available from controlled trials to guide a clinician in the longer-term management of a patient who improves during treatment of an acute manic episode with RISPERDAL. While it is generally agreed that pharmacological treatment beyond an acute response in mania is desirable, both for maintenance of the initial response and for prevention of new manic episodes, there are no systematically obtained data to support the use of RISPERDAL in such longer-term treatment (i.e., beyond 3 weeks). The physician who elects to use RISPERDAL for extended periods should periodically re-evaluate the long-term risks and benefits of the drug for the individual patient.

2.3 Irritability Associated with Autistic Disorder – Pediatrics (Children and Adolescents)

The dosage of RISPERDAL should be individualized according to the response and tolerability of the patient. The total daily dose of RISPERDAL can be administered once daily, or half the total daily dose can be administered twice daily.

For patients with body weight less than 20 kg, initiate dosing at 0.25 mg per day. For patients with body weight greater than or equal to 20 kg, initiate dosing at 0.5 mg per day. After a minimum of four days, the dose may be increased to the recommended dose of 0.5 mg per day for patients less than 20 kg and 1.0 mg per day for patients greater than or equal to 20 kg. Maintain this dose for a minimum of 14 days. In patients not achieving sufficient clinical response, the dose may be increased at intervals of 2 weeks or greater, in increments of 0.25 mg per day for patients less than 20 kg, or increments of 0.5 mg per day for patients greater than or equal to 20 kg. The effective dose range is 0.5 mg to 3 mg per day. No dosing data are available for children who weigh less than 15 kg.

Once sufficient clinical response has been achieved and maintained, consider gradually lowering the dose to achieve the optimal balance of efficacy and safety. The physician who elects to use RISPERDAL for extended periods should periodically re-evaluate the long-term risks and benefits of the drug for the individual patient.

Patients experiencing persistent somnolence may benefit from a once-daily dose administered at bedtime or administering half the daily dose twice daily, or a reduction of the dose.

2.4 Dosing in Patients with Severe Renal or Hepatic Impairment

For patients with severe renal impairment (Clcr< 30 mL/min) or hepatic impairment (10–15 points on Child Pugh System), the initial starting dose is 0.5 mg twice daily. The dose may be increased in increments of 0.5 mg or less, administered twice daily. For doses above 1.5 mg twice daily, increase in intervals of one week or greater [see Use in Specific Populations (8.6 and 8.7)].

2.5 Dose Adjustments for Specific Drug Interactions

When RISPERDAL is co-administered with enzyme inducers (e.g., carbamazepine), the dose of RISPERDAL should be increased up to double the patient's usual dose. It may be necessary to decrease the RISPERDAL dose when enzyme inducers such as carbamazepine are discontinued [see Drug Interactions (7.1)] . Similar effect may be expected with co-administration of RISPERDAL with other enzyme inducers (e.g., phenytoin, rifampin, and phenobarbital).

When fluoxetine or paroxetine is co-administered with RISPERDAL, the dose of RISPERDAL should be reduced. The RISPERDAL dose should not exceed 8 mg per day in adults when co-administered with these drugs. When initiating therapy, RISPERDAL should be titrated slowly. It may be necessary to increase the RISPERDAL dose when enzyme inhibitors such as fluoxetine or paroxetine are discontinued [see Drug Interactions (7.1)] .

2.6 Administration of RISPERDAL Oral Solution

RISPERDAL Oral Solution can be administered directly from the calibrated oral dosing syringe, or can be mixed with a beverage prior to administration. RISPERDAL Oral Solution is compatible in the following beverages: water, coffee, orange juice, and low-fat milk; it is NOT compatible with either cola or tea.

2.7 Directions for Use of RISPERDAL M-TAB Orally Disintegrating Tablets

Tablet Accessing

RISPERDAL M-TAB Orally Disintegrating Tablets 0.5 mg, 1 mg, and 2 mg

RISPERDAL M-TAB Orally Disintegrating Tablets 0.5 mg, 1 mg, and 2 mg are supplied in blister packs of 4 tablets each.

Do not open the blister until ready to administer. For single tablet removal, separate one of the four blister units by tearing apart at the perforations. Bend the corner where indicated. Peel back foil to expose the tablet. DO NOT push the tablet through the foil because this could damage the tablet.

RISPERDAL M-TAB Orally Disintegrating Tablets 3 mg and 4 mg

RISPERDAL M-TAB Orally Disintegrating Tablets 3 mg and 4 mg are supplied in a child-resistant pouch containing a blister with 1 tablet each.

The child-resistant pouch should be torn open at the notch to access the blister. Do not open the blister until ready to administer. Peel back foil from the side to expose the tablet. DO NOT push the tablet through the foil, because this could damage the tablet.

Tablet Administration

Using dry hands, remove the tablet from the blister unit and immediately place the entire RISPERDAL M-TAB Orally Disintegrating Tablet on the tongue. The RISPERDAL M-TAB Orally Disintegrating Tablet should be consumed immediately, as the tablet cannot be stored once removed from the blister unit. RISPERDAL M-TAB Orally Disintegrating Tablets disintegrate in the mouth within seconds and can be swallowed subsequently with or without liquid. Patients should not attempt to split or to chew the tablet.

3 DOSAGE FORMS AND STRENGTHS

RISPERDAL Tablets are available in the following strengths and colors: 0.5 mg (red-brown), 1 mg (white), 2 mg (orange), 3 mg (yellow), and 4 mg (green). All are capsule shaped, and imprinted with "JANSSEN" on one side and either "Ris 0.5", "R1", "R2", "R3", or "R4" on the other side according to their respective strengths.

RISPERDAL Oral Solution is available in a 1 mg/mL strength.

RISPERDAL M-TAB Orally Disintegrating Tablets are available in the following strengths, colors, and shapes: 0.5 mg (light coral, round), 1 mg (light coral, square), 2 mg (coral, square), 3 mg (coral, round), and 4 mg (coral, round). All are biconvex and etched on one side with "R0.5", "R1", "R2", "R3", or "R4" according to their respective strengths.

4 CONTRAINDICATIONS

RISPERDAL is contraindicated in patients with a known hypersensitivity to either risperidone or paliperidone, or to any of the excipients in the RISPERDAL formulation. Hypersensitivity reactions, including anaphylactic reactions and angioedema, have been reported in patients treated with risperidone and in patients treated with paliperidone. Paliperidone is a metabolite of risperidone.

5 WARNINGS AND PRECAUTIONS

5.1 Increased Mortality in Elderly Patients with Dementia-Related Psychosis

Elderly patients with dementia-related psychosis treated with antipsychotic drugs are at an increased risk of death. Analyses of 17 placebo-controlled trials (modal duration of 10 weeks), largely in patients taking atypical antipsychotic drugs, revealed a risk of death in drug-treated patients of between 1.6 to 1.7 times the risk of death in placebo-treated patients. Over the course of a typical 10-week controlled trial, the rate of death in drug-treated patients was about 4.5%, compared to a rate of about 2.6% in the placebo group. Although the causes of death were varied, most of the deaths appeared to be either cardiovascular (e.g., heart failure, sudden death) or infectious (e.g., pneumonia) in nature. Observational studies suggest that, similar to atypical antipsychotic drugs, treatment with conventional antipsychotic drugs may increase mortality. The extent to which the findings of increased mortality in observational studies may be attributed to the antipsychotic drug as opposed to some characteristic(s) of the patients is not clear.

In two of four placebo-controlled trials in elderly patients with dementia-related psychosis, a higher incidence of mortality was observed in patients treated with furosemide plus RISPERDAL when compared to patients treated with RISPERDAL alone or with placebo plus furosemide. No pathological mechanism has been identified to explain this finding, and no consistent pattern for cause of death was observed.

RISPERDAL (risperidone) is not approved for the treatment of dementia-related psychosis [see Boxed Warning] .

5.2 Cerebrovascular Adverse Reactions, Including Stroke, in Elderly Patients with Dementia-Related Psychosis

Cerebrovascular adverse reactions (e.g., stroke, transient ischemic attack), including fatalities, were reported in patients (mean age 85 years; range 73–97) in trials of risperidone in elderly patients with dementia-related psychosis. In placebo-controlled trials, there was a significantly higher incidence of cerebrovascular adverse events in patients treated with risperidone compared to patients treated with placebo. RISPERDAL is not approved for the treatment of patients with dementia-related psychosis. [see Boxed Warningand Warnings and Precautions (5.1)].

5.3 Neuroleptic Malignant Syndrome

Neuroleptic Malignant Syndrome (NMS), a potentially fatal symptom complex, has been reported in association with antipsychotic drugs. Clinical manifestations of NMS are hyperpyrexia, muscle rigidity, altered mental status including delirium, and autonomic instability (irregular pulse or blood pressure, tachycardia, diaphoresis, and cardiac dysrhythmia). Additional signs may include elevated creatine phosphokinase, myoglobinuria (rhabdomyolysis), and acute renal failure.

If NMS is suspected, immediately discontinue RISPERDAL and provide symptomatic treatment and monitoring.

5.4 Tardive Dyskinesia

Tardive dyskinesia, a syndrome consisting of potentially irreversible, involuntary, dyskinetic movements, may develop in patients treated with antipsychotic drugs. Although the prevalence of the syndrome appears to be highest among the elderly, especially elderly women, it is impossible to predict which patients will develop the syndrome. Whether antipsychotic drug products differ in their potential to cause tardive dyskinesia is unknown.

The risk of developing tardive dyskinesia and the likelihood that it will become irreversible increase with the duration of treatment and the cumulative dose. The syndrome can develop after relatively brief treatment periods, even at low doses. It may also occur after discontinuation of treatment.

Tardive dyskinesia may remit, partially or completely, if antipsychotic treatment is discontinued. Antipsychotic treatment, itself, however, may suppress (or partially suppress) the signs and symptoms of the syndrome, possibly masking the underlying process. The effect that symptomatic suppression has upon the long-term course of the syndrome is unknown.

Given these considerations, RISPERDAL should be prescribed in a manner that is most likely to minimize the occurrence of tardive dyskinesia. Chronic antipsychotic treatment should generally be reserved for patients: (1) who suffer from a chronic illness that is known to respond to antipsychotic drugs, and (2) for whom alternative, equally effective, but potentially less harmful treatments are not available or appropriate. In patients who do require chronic treatment, use the lowest dose and the shortest duration of treatment producing a satisfactory clinical response. Periodically reassess the need for continued treatment.

If signs and symptoms of tardive dyskinesia appear in a patient on RISPERDAL, drug discontinuation should be considered. However, some patients may require treatment with RISPERDAL despite the presence of the syndrome.

5.5 Metabolic Changes

Atypical antipsychotic drugs have been associated with metabolic changes that may increase cardiovascular/cerebrovascular risk. These metabolic changes include hyperglycemia, dyslipidemia, and body weight gain. While all of the drugs in the class have been shown to produce some metabolic changes, each drug has its own specific risk profile.

Hyperglycemia and Diabetes Mellitus

Hyperglycemia and diabetes mellitus, in some cases extreme and associated with ketoacidosis or hyperosmolar coma or death, have been reported in patients treated with atypical antipsychotics including RISPERDAL. Assessment of the relationship between atypical antipsychotic use and glucose abnormalities is complicated by the possibility of an increased background risk of diabetes mellitus in patients with schizophrenia and the increasing incidence of diabetes mellitus in the general population. Given these confounders, the relationship between atypical antipsychotic use and hyperglycemia-related adverse events is not completely understood. However, epidemiological studies suggest an increased risk of treatment-emergent hyperglycemia-related adverse events in patients treated with the atypical antipsychotics. Precise risk estimates for hyperglycemia-related adverse events in patients treated with atypical antipsychotics are not available.

Patients with an established diagnosis of diabetes mellitus who are started on atypical antipsychotics, including RISPERDAL, should be monitored regularly for worsening of glucose control. Patients with risk factors for diabetes mellitus (e.g., obesity, family history of diabetes) who are starting treatment with atypical antipsychotics, including RISPERDAL, should undergo fasting blood glucose testing at the beginning of treatment and periodically during treatment. Any patient treated with atypical antipsychotics, including RISPERDAL, should be monitored for symptoms of hyperglycemia including polydipsia, polyuria, polyphagia, and weakness. Patients who develop symptoms of hyperglycemia during treatment with atypical antipsychotics, including RISPERDAL, should undergo fasting blood glucose testing. In some cases, hyperglycemia has resolved when the atypical antipsychotic, including RISPERDAL, was discontinued; however, some patients required continuation of anti-diabetic treatment despite discontinuation of RISPERDAL.

Pooled data from three double-blind, placebo-controlled schizophrenia studies and four double-blind, placebo-controlled bipolar monotherapy studies are presented in Table 2.

Table 2. Change in Random Glucose from Seven Placebo-Controlled, 3- to 8-Week, Fixed- or Flexible-Dose Studies in Adult Subjects with Schizophrenia or Bipolar Mania
 |  | RISPERDAL
 | Placebo | 1–8 mg/day | >8–16 mg/day
 | Mean change from baseline (mg/dL)
 | n=555 | n=748 | n=164
Serum Glucose | -1.4 | 0.8 | 0.6
 | Proportion of patients with shifts
Serum Glucose (<140 mg/dL to ≥200 mg/dL) | 0.6% (3/525) | 0.4% (3/702) | 0% (0/158)

In longer-term, controlled and uncontrolled studies, RISPERDAL was associated with a mean change in glucose of +2.8 mg/dL at Week 24 (n=151) and +4.1 mg/dL at Week 48 (n=50).

Data from the placebo-controlled 3- to 6-week study in children and adolescents with schizophrenia (13–17 years of age), bipolar mania (10–17 years of age), or autistic disorder (5 to 17 years of age) are presented in Table 3.

Table 3. Change in Fasting Glucose from Three Placebo-Controlled, 3- to 6-Week, Fixed-Dose Studies in Children and Adolescents with Schizophrenia (13–17 years of age), Bipolar Mania (10–17 years of age), or Autistic Disorder (5 to 17 years of age)
 |  | RISPERDAL
 | Placebo | 0.5–6 mg/day
 | Mean change from baseline (mg/dL)
 | n=76 | n=135
Serum Glucose | -1.3 | 2.6
 | Proportion of patients with shifts
Serum Glucose (<100 mg/dL to ≥126 mg/dL) | 0% (0/64) | 0.8% (1/120)

In longer-term, uncontrolled, open-label extension pediatric studies, RISPERDAL was associated with a mean change in fasting glucose of +5.2 mg/dL at Week 24 (n=119).

Dyslipidemia

Undesirable alterations in lipids have been observed in patients treated with atypical antipsychotics.

Pooled data from 7 placebo-controlled, 3- to 8- week, fixed- or flexible-dose studies in adult subjects with schizophrenia or bipolar mania are presented in Table 4.

Table 4. Change in Random Lipids from Seven Placebo-Controlled, 3- to 8-Week, Fixed- or Flexible-Dose Studies in Adult Subjects with Schizophrenia or Bipolar Mania
 |  | RISPERDAL
 | Placebo | 1–8 mg/day | >8–16 mg/day
 | Mean change from baseline (mg/dL)
Cholesterol | n=559 | n=742 | n=156
Change from baseline | 0.6 | 6.9 | 1.8
Triglycerides | n=183 | n=307 | n=123
Change from baseline | -17.4 | -4.9 | -8.3
 | Proportion of patients With Shifts
Cholesterol (<200 mg/dL to ≥240 mg/dL) | 2.7% | 4.3% | 6.3%
 | (10/368) | (22/516) | (6/96)
Triglycerides (<500 mg/dL to ≥500 mg/dL) | 1.1% (2/180) | 2.7% (8/301) | 2.5% (3/121)

In longer-term, controlled and uncontrolled studies, RISPERDAL was associated with a mean change in (a) non-fasting cholesterol of +4.4 mg/dL at Week 24 (n=231) and +5.5 mg/dL at Week 48 (n=86); and (b) non-fasting triglycerides of +19.9 mg/dL at Week 24 (n=52).

Pooled data from 3 placebo-controlled, 3- to 6-week, fixed-dose studies in children and adolescents with schizophrenia (13–17 years of age), bipolar mania (10–17 years of age), or autistic disorder (5–17 years of age) are presented in Table 5.

Table 5. Change in Fasting Lipids from Three Placebo-Controlled, 3- to 6-Week, Fixed-Dose Studies in Children and Adolescents with Schizophrenia (13–17 Years of Age), Bipolar Mania (10–17 Years of Age), or Autistic Disorder (5 to 17 Years of Age)
 |  | RISPERDAL
 | Placebo | 0.5–6 mg/day
 | Mean change from baseline (mg/dL)
Cholesterol | n=74 | n=133
Change from baseline | 0.3 | -0.3
LDL | n=22 | n=22
Change from baseline | 3.7 | 0.5
HDL | n=22 | n=22
Change from baseline | 1.6 | -1.9
Triglycerides | n=77 | n=138
Change from baseline | -9.0 | -2.6
 | Proportion of patients with shifts
Cholesterol (<170 mg/dL to ≥200 mg/dL) | 2.4% (1/42) | 3.8% (3/80)
LDL (<110 mg/dL to ≥130 mg/dL) | 0% (0/16) | 0% (0/16)
HDL (≥40 mg/dL to <40 mg/dL) | 0% (0/19) | 10% (2/20)
Triglycerides (<150 mg/dL to ≥200 mg/dL) | 1.5% (1/65) | 7.1% (8/113)

In longer-term, uncontrolled, open-label extension pediatric studies, RISPERDAL was associated with a mean change in (a) fasting cholesterol of +2.1 mg/dL at Week 24 (n=114); (b) fasting LDL of -0.2 mg/dL at Week 24 (n=103); (c) fasting HDL of +0.4 mg/dL at Week 24 (n=103); and (d) fasting triglycerides of +6.8 mg/dL at Week 24 (n=120).

Weight Gain

Weight gain has been observed with atypical antipsychotic use. Clinical monitoring of weight is recommended.

Data on mean changes in body weight and the proportion of subjects meeting a weight gain criterion of 7% or greater of body weight from 7 placebo-controlled, 3- to 8- week, fixed- or flexible-dose studies in adult subjects with schizophrenia or bipolar mania are presented in Table 6.

Table 6. Mean Change in Body Weight (kg) and the Proportion of Subjects with ≥7% Gain in Body Weight From Seven Placebo-Controlled, 3- to 8-Week, Fixed- or Flexible-Dose Studies in Adult Subjects With Schizophrenia or Bipolar Mania
 |  | RISPERDAL
 | Placebo (n=597) | 1–8 mg/day (n=769) | >8–16 mg/day (n=158)
Weight (kg)
Change from baseline | -0.3 | 0.7 | 2.2
Weight Gain
≥7% increase from baseline | 2.9% | 8.7% | 20.9%

In longer-term, controlled and uncontrolled studies, RISPERDAL was associated with a mean change in weight of +4.3 kg at Week 24 (n=395) and +5.3 kg at Week 48 (n=203).

Data on mean changes in body weight and the proportion of subjects meeting the criterion of ≥7% gain in body weight from nine placebo-controlled, 3- to 8-week, fixed-dose studies in children and adolescents with schizophrenia (13–17 years of age), bipolar mania (10–17 years of age), autistic disorder (5–17 years of age), or other psychiatric disorders (5–17 years of age) are presented in Table 7.

Table 7. Mean Change in Body Weight (kg) and the Proportion of Subjects With ≥7% Gain in Body Weight From Nine Placebo-Controlled, 3- to 8-Week, Fixed-Dose Studies in Children and Adolescents With Schizophrenia (13–17 Years of Age), Bipolar Mania (10–17 Years of Age), Autistic Disorder (5 to 17 Years of Age) or Other Psychiatric Disorders (5–17 Years of Age)
 | Placebo (n=375) | RISPERDAL 0.5–6 mg/day (n=448)
Weight (kg)
Change from baseline | 0.6 | 2.0
Weight Gain
≥7% increase from baseline | 6.9% | 32.6%

In longer-term, uncontrolled, open-label extension pediatric studies, RISPERDAL was associated with a mean change in weight of +5.5 kg at Week 24 (n=748) and +8.0 kg at Week 48 (n=242).

In a long-term, open-label extension study in adolescent patients with schizophrenia, weight increase was reported as a treatment-emergent adverse event in 14% of patients. In 103 adolescent patients with schizophrenia, a mean increase of 9.0 kg was observed after 8 months of RISPERDAL treatment. The majority of that increase was observed within the first 6 months. The average percentiles at baseline and 8 months, respectively, were 56 and 72 for weight, 55 and 58 for height, and 51 and 71 for body mass index.

In long-term, open-label trials (studies in patients with autistic disorder or other psychiatric disorders), a mean increase of 7.5 kg after 12 months of RISPERDAL treatment was observed, which was higher than the expected normal weight gain (approximately 3 to 3.5 kg per year adjusted for age, based on Centers for Disease Control and Prevention normative data). The majority of that increase occurred within the first 6 months of exposure to RISPERDAL. The average percentiles at baseline and 12 months, respectively, were 49 and 60 for weight, 48 and 53 for height, and 50 and 62 for body mass index.

In one 3-week, placebo-controlled trial in children and adolescent patients with acute manic or mixed episodes of bipolar I disorder, increases in body weight were higher in the RISPERDAL groups than the placebo group, but not dose related (1.90 kg in the RISPERDAL 0.5–2.5 mg group, 1.44 kg in the RISPERDAL 3–6 mg group, and 0.65 kg in the placebo group). A similar trend was observed in the mean change from baseline in body mass index.

When treating pediatric patients with RISPERDAL for any indication, weight gain should be assessed against that expected with normal growth.

5.6 Hyperprolactinemia

As with other drugs that antagonize dopamine D2receptors, RISPERDAL elevates prolactin levels and the elevation persists during chronic administration. RISPERDAL is associated with higher levels of prolactin elevation than other antipsychotic agents.

Hyperprolactinemia may suppress hypothalamic GnRH, resulting in reduced pituitary gonadotropin secretion. This, in turn, may inhibit reproductive function by impairing gonadal steroidogenesis in both female and male patients. Galactorrhea, amenorrhea, gynecomastia, and impotence have been reported in patients receiving prolactin-elevating compounds. Long-standing hyperprolactinemia when associated with hypogonadism may lead to decreased bone density in both female and male subjects.

Tissue culture experiments indicate that approximately one-third of human breast cancers are prolactin dependent in vitro, a factor of potential importance if the prescription of these drugs is contemplated in a patient with previously detected breast cancer. An increase in pituitary gland, mammary gland, and pancreatic islet cell neoplasia (mammary adenocarcinomas, pituitary and pancreatic adenomas) was observed in the risperidone carcinogenicity studies conducted in mice and rats [see Nonclinical Toxicology (13.1)] . Published epidemiologic studies have shown inconsistent results when exploring the potential association between hyperprolactinemia and breast cancer.

5.7 Orthostatic Hypotension

RISPERDAL may induce orthostatic hypotension associated with dizziness, tachycardia, and in some patients, syncope, especially during the initial dose-titration period, probably reflecting its alpha-adrenergic antagonistic properties. Syncope was reported in 0.2% (6/2607) of RISPERDAL-treated patients in Phase 2 and 3 studies in adults with schizophrenia. The risk of orthostatic hypotension and syncope may be minimized by limiting the initial dose to 2 mg total (either once daily or 1 mg twice daily) in normal adults and 0.5 mg twice daily in the elderly and patients with renal or hepatic impairment [see Dosage and Administration (2.1, 2.4)] . Monitoring of orthostatic vital signs should be considered in patients for whom this is of concern. A dose reduction should be considered if hypotension occurs. RISPERDAL should be used with particular caution in patients with known cardiovascular disease (history of myocardial infarction or ischemia, heart failure, or conduction abnormalities), cerebrovascular disease, and conditions which would predispose patients to hypotension, e.g., dehydration and hypovolemia, and in the elderly and patients with renal or hepatic impairment. Monitoring of orthostatic vital signs should be considered if hypotension occurs. Clinically significant hypotension has been observed with concomitant use of RISPERDAL and antihypertensive medication.

5.8 Falls

Somnolence, postural hypotension, motor and sensory instability have been reported with the use of antipsychotics, including RISPERDAL, which may lead to falls and, consequently, fractures or other fall-related injuries. For patients, particularly the elderly, with diseases, conditions, or medications that could exacerbate these effects, assess the risk of falls when initiating antipsychotic treatment and recurrently for patients on long-term antipsychotic therapy.

5.9 Leukopenia, Neutropenia, and Agranulocytosis

Class Effect:In clinical trial and/or postmarketing experience, events of leukopenia/neutropenia have been reported temporally related to antipsychotic agents, including RISPERDAL. Agranulocytosis has also been reported.

Possible risk factors for leukopenia/neutropenia include pre-existing low white blood cell count (WBC) and history of drug-induced leukopenia/neutropenia. Patients with a history of a clinically significant low WBC or a drug-induced leukopenia/neutropenia should have their complete blood count (CBC) monitored frequently during the first few months of therapy and discontinuation of RISPERDAL should be considered at the first sign of a clinically significant decline in WBC in the absence of other causative factors.

Patients with clinically significant neutropenia should be carefully monitored for fever or other symptoms or signs of infection and treated promptly if such symptoms or signs occur. Patients with severe neutropenia (absolute neutrophil count <1000/mm^3) should discontinue RISPERDAL and have their WBC followed until recovery.

5.10 Potential for Cognitive and Motor Impairment

Somnolence was a commonly reported adverse reaction associated with RISPERDAL treatment, especially when ascertained by direct questioning of patients. This adverse reaction is dose-related, and in a study utilizing a checklist to detect adverse events, 41% of the high-dose patients (RISPERDAL 16 mg/day) reported somnolence compared to 16% of placebo patients. Direct questioning is more sensitive for detecting adverse events than spontaneous reporting, by which 8% of RISPERDAL 16 mg/day patients and 1% of placebo patients reported somnolence as an adverse reaction. Since RISPERDAL has the potential to impair judgment, thinking, or motor skills, patients should be cautioned about operating hazardous machinery, including automobiles, until they are reasonably certain that RISPERDAL therapy does not affect them adversely.

5.11 Seizures

During premarketing testing in adult patients with schizophrenia, seizures occurred in 0.3% (9/2607) of RISPERDAL-treated patients, two in association with hyponatremia. RISPERDAL should be used cautiously in patients with a history of seizures.

5.12 Dysphagia

Esophageal dysmotility and aspiration have been associated with antipsychotic drug use. Aspiration pneumonia is a common cause of morbidity and mortality in patients with advanced Alzheimer's dementia. RISPERDAL and other antipsychotic drugs should be used cautiously in patients at risk for aspiration pneumonia. [see Boxed Warningand Warnings and Precautions (5.1)] .

5.13 Priapism

Priapism has been reported during postmarketing surveillance. Severe priapism may require surgical intervention.

5.14 Body Temperature Regulation

Disruption of body temperature regulation has been attributed to antipsychotic agents. Both hyperthermia and hypothermia have been reported in association with oral RISPERDAL use. Caution is advised when prescribing for patients who will be exposed to temperature extremes.

5.15 Patients with Phenylketonuria

Inform patients that RISPERDAL M-TAB Orally Disintegrating Tablets contain phenylalanine. Phenylalanine is a component of aspartame. Each 4 mg RISPERDAL M-TAB Orally Disintegrating Tablet contains 0.84 mg phenylalanine; each 3 mg RISPERDAL M-TAB Orally Disintegrating Tablet contains 0.63 mg phenylalanine; each 2 mg RISPERDAL M-TAB Orally Disintegrating Tablet contains 0.42 mg phenylalanine; each 1 mg RISPERDAL M-TAB Orally Disintegrating Tablet contains 0.28 mg phenylalanine; and each 0.5 mg RISPERDAL M-TAB Orally Disintegrating Tablet contains 0.14 mg phenylalanine.

6 ADVERSE REACTIONS

The following are discussed in more detail in other sections of the labeling:

- Increased mortality in elderly patients with dementia-related psychosis [see Boxed Warningand Warnings and Precautions (5.1)]
- Cerebrovascular adverse events, including stroke, in elderly patients with dementia-related psychosis [see Warnings and Precautions (5.2)]
- Neuroleptic malignant syndrome [see Warnings and Precautions (5.3)]
- Tardive dyskinesia [see Warnings and Precautions (5.4)]
- Metabolic Changes (Hyperglycemia and diabetes mellitus, Dyslipidemia, and Weight Gain) [see Warnings and Precautions (5.5)]
- Hyperprolactinemia [see Warnings and Precautions (5.6)]
- Orthostatic hypotension [see Warnings and Precautions (5.7)]
- Falls [see Warnings and Precautions (5.8)]
- Leukopenia, neutropenia, and agranulocytosis [see Warnings and Precautions (5.9)]
- Potential for cognitive and motor impairment [see Warnings and Precautions (5.10)]
- Seizures [see Warnings and Precautions (5.11)]
- Dysphagia [see Warnings and Precautions (5.12)]
- Priapism [see Warnings and Precautions (5.13)]
- Disruption of body temperature regulation [see Warnings and Precautions (5.14)]
- Patients with Phenylketonuria [see Warnings and Precautions (5.15)].

The most common adverse reactions in clinical trials (>5% and twice placebo) were parkinsonism, akathisia, dystonia, tremor, sedation, dizziness, anxiety, blurred vision, nausea, vomiting, upper abdominal pain, stomach discomfort, dyspepsia, diarrhea, salivary hypersecretion, constipation, dry mouth, increased appetite, increased weight, fatigue, rash, nasal congestion, upper respiratory tract infection, nasopharyngitis, and pharyngolaryngeal pain.

The most common adverse reactions that were associated with discontinuation from clinical trials (causing discontinuation in >1% of adults and/or >2% of pediatrics) were nausea, somnolence, sedation, vomiting, dizziness, and akathisia [see Adverse Reactions, Discontinuations Due to Adverse Reactions (6.1)] .

The data described in this section are derived from a clinical trial database consisting of 9803 adult and pediatric patients exposed to one or more doses of RISPERDAL for the treatment of schizophrenia, bipolar mania, autistic disorder, and other psychiatric disorders in pediatrics and elderly patients with dementia. Of these 9803 patients, 2687 were patients who received RISPERDAL while participating in double-blind, placebo-controlled trials. The conditions and duration of treatment with RISPERDAL varied greatly and included (in overlapping categories) double-blind, fixed- and flexible-dose, placebo- or active-controlled studies and open-label phases of studies, inpatients and outpatients, and short-term (up to 12 weeks) and longer-term (up to 3 years) exposures. Safety was assessed by collecting adverse events and performing physical examinations, vital signs, body weights, laboratory analyses, and ECGs.

6.1 Clinical Trials Experience

Because clinical trials are conducted under widely varying conditions, adverse reaction rates observed in the clinical trials of a drug cannot be directly compared to rates in the clinical trials of another drug and may not reflect the rates observed in clinical practice.

Commonly-Observed Adverse Reactions in Double-Blind, Placebo-Controlled Clinical Trials – Schizophrenia

Adult Patients with Schizophrenia

Table 8 lists the adverse reactions reported in 2% or more of RISPERDAL-treated adult patients with schizophrenia in three 4- to 8-week, double-blind, placebo-controlled trials.

Table 8. Adverse Reactions in ≥2% of RISPERDAL-Treated Adult Patients (and greater than placebo) with Schizophrenia in Double-Blind, Placebo-Controlled Trials
 | Percentage of Patients Reporting Reaction
 | RISPERDAL
System/Organ Class Adverse Reaction | 2–8 mg per day (N=366) | >8–16 mg per day (N=198) | Placebo (N=225)
Cardiac Disorders
Tachycardia | 1 | 3 | 0
Eye Disorders
Vision blurred | 3 | 1 | 1
Gastrointestinal Disorders
Nausea | 9 | 4 | 4
Constipation | 8 | 9 | 6
Dyspepsia | 8 | 6 | 5
Dry mouth | 4 | 0 | 1
Abdominal discomfort | 3 | 1 | 1
Salivary hypersecretion | 2 | 1 | <1
Diarrhea | 2 | 1 | 1
General Disorders
Fatigue | 3 | 1 | 0
Chest pain | 2 | 2 | 1
Asthenia | 2 | 1 | <1
Infections and Infestations
Nasopharyngitis | 3 | 4 | 3
Upper respiratory tract infection | 2 | 3 | 1
Sinusitis | 1 | 2 | 1
Urinary tract infection | 1 | 3 | 0
Investigations
Blood creatine phosphokinase increased | 1 | 2 | <1
Heart rate increased | <1 | 2 | 0
Musculoskeletal and Connective Tissue Disorders
Back pain | 4 | 1 | 1
Arthralgia | 2 | 3 | <1
Pain in extremity | 2 | 1 | 1
Nervous System Disorders
Parkinsonism [Parkinsonism includes extrapyramidal disorder, musculoskeletal stiffness, parkinsonism, cogwheel rigidity, akinesia, bradykinesia, hypokinesia, masked facies, muscle rigidity, and Parkinson's disease. Akathisia includes akathisia and restlessness. Dystonia includes dystonia, muscle spasms, muscle contractions involuntary, muscle contracture, oculogyration, tongue paralysis. Tremor includes tremor and parkinsonian rest tremor.] | 14 | 17 | 8
Akathisia | 10 | 10 | 3
Sedation | 10 | 5 | 2
Dizziness | 7 | 4 | 2
Dystonia | 3 | 4 | 2
Tremor | 2 | 3 | 1
Dizziness postural | 2 | 0 | 0
Psychiatric Disorders
Insomnia | 32 | 25 | 27
Anxiety | 16 | 11 | 11
Respiratory, Thoracic and Mediastinal Disorders
Nasal congestion | 4 | 6 | 2
Dyspnea | 1 | 2 | 0
Epistaxis | <1 | 2 | 0
Skin and Subcutaneous Tissue Disorders
Rash | 1 | 4 | 1
Dry skin | 1 | 3 | 0
Vascular Disorders
Orthostatic hypotension | 2 | 1 | 0

Pediatric Patients with Schizophrenia

Table 9 lists the adverse reactions reported in 5% or more of RISPERDAL-treated pediatric patients with schizophrenia in a 6-week double-blind, placebo-controlled trial.

Table 9. Adverse Reactions in ≥5% of RISPERDAL-Treated Pediatric Patients (and greater than placebo) with Schizophrenia in a Double-Blind Trial
 | Percentage of Patients Reporting Reaction
 | RISPERDAL
System/Organ Class Adverse Reaction | 1–3 mg per day (N=55) | 4–6 mg per day (N=51) | Placebo (N=54)
Gastrointestinal Disorders
Salivary hypersecretion | 0 | 10 | 2
Nervous System Disorders
Sedation | 24 | 12 | 4
Parkinsonism [Parkinsonism includes extrapyramidal disorder, muscle rigidity, musculoskeletal stiffness, and hypokinesia. Akathisia includes akathisia and restlessness. Dystonia includes dystonia and oculogyration.] | 16 | 28 | 11
Tremor | 11 | 10 | 6
Akathisia | 9 | 10 | 4
Dizziness | 7 | 14 | 2
Dystonia | 2 | 6 | 0
Psychiatric Disorders
Anxiety | 7 | 6 | 0

Commonly-Observed Adverse Reactions in Double-Blind, Placebo-Controlled Clinical Trials – Bipolar Mania

Adult Patients with Bipolar Mania

Table 10 lists the adverse reactions reported in 2% or more of RISPERDAL-treated adult patients with bipolar mania in four 3-week, double-blind, placebo-controlled monotherapy trials.

Table 10. Adverse Reactions in ≥2% of RISPERDAL-Treated Adult Patients (and greater than placebo) with Bipolar Mania in Double-Blind, Placebo-Controlled Monotherapy Trials
 | Percentage of Patients Reporting Reaction
System/Organ Class Adverse Reaction | RISPERDAL 1–6 mg per day (N=448) | Placebo (N=424)
Eye Disorders
Vision blurred | 2 | 1
Gastrointestinal Disorders
Nausea | 5 | 2
Diarrhea | 3 | 2
Salivary hypersecretion | 3 | 1
Stomach discomfort | 2 | <1
General Disorders
Fatigue | 2 | 1
Nervous System Disorders
Parkinsonism [Parkinsonism includes extrapyramidal disorder, parkinsonism, musculoskeletal stiffness, hypokinesia, muscle rigidity, muscle tightness, bradykinesia, cogwheel rigidity. Akathisia includes akathisia and restlessness. Tremor includes tremor and parkinsonian rest tremor. Dystonia includes dystonia, muscle spasms, oculogyration, torticollis.] | 25 | 9
Sedation | 11 | 4
Akathisia | 9 | 3
Tremor | 6 | 3
Dizziness | 6 | 5
Dystonia | 5 | 1
Lethargy | 2 | 1

Table 11 lists the adverse reactions reported in 2% or more of RISPERDAL-treated adult patients with bipolar mania in two 3-week, double-blind, placebo-controlled adjuvant therapy trials.

Table 11. Adverse Reactions in ≥2% of RISPERDAL-Treated Adult Patients (and greater than placebo) with Bipolar Mania in Double-Blind, Placebo-Controlled Adjunctive Therapy Trials
 | Percentage of Patients Reporting Reaction
System/Organ Class | RISPERDAL + Mood Stabilizer | Placebo + Mood Stabilizer
Adverse Reaction | (N=127) | (N=126)
Cardiac Disorders
Palpitations | 2 | 0
Gastrointestinal Disorders
Dyspepsia | 9 | 8
Nausea | 6 | 4
Diarrhea | 6 | 4
Salivary hypersecretion | 2 | 0
General Disorders
Chest pain | 2 | 1
Infections and Infestations
Urinary tract infection | 2 | 1
Nervous System Disorders
Parkinsonism [Parkinsonism includes extrapyramidal disorder, hypokinesia and bradykinesia. Akathisia includes hyperkinesia and akathisia.] | 14 | 4
Sedation | 9 | 4
Akathisia | 8 | 0
Dizziness | 7 | 2
Tremor | 6 | 2
Lethargy | 2 | 1
Psychiatric Disorders
Anxiety | 3 | 2
Respiratory, Thoracic and Mediastinal Disorders
Pharyngolaryngeal pain | 5 | 2
Cough | 2 | 0

Pediatric Patients with Bipolar Mania

Table 12 lists the adverse reactions reported in 5% or more of RISPERDAL-treated pediatric patients with bipolar mania in a 3-week double-blind, placebo-controlled trial.

Table 12. Adverse Reactions in ≥5% of RISPERDAL-Treated Pediatric Patients (and greater than placebo) with Bipolar Mania in Double-Blind, Placebo-Controlled Trials
 | Percentage of Patients Reporting Reaction
 | RISPERDAL
System/Organ Class Adverse Reaction | 0.5–2.5 mg per day (N=50) | 3–6 mg per day (N=61) | Placebo (N=58)
Eye Disorders
Vision blurred | 4 | 7 | 0
Gastrointestinal Disorders
Abdominal pain upper | 16 | 13 | 5
Nausea | 16 | 13 | 7
Vomiting | 10 | 10 | 5
Diarrhea | 8 | 7 | 2
Dyspepsia | 10 | 3 | 2
Stomach discomfort | 6 | 0 | 2
General Disorders
Fatigue | 18 | 30 | 3
Metabolism and Nutrition Disorders
Increased appetite | 4 | 7 | 2
Nervous System Disorders
Sedation | 42 | 56 | 19
Dizziness | 16 | 13 | 5
Parkinsonism [Parkinsonism includes musculoskeletal stiffness, extrapyramidal disorder, bradykinesia, and nuchal rigidity. Dystonia includes dystonia, laryngospasm, and muscle spasms. Akathisia includes restlessness and akathisia.] | 6 | 12 | 3
Dystonia | 6 | 5 | 0
Akathisia | 0 | 8 | 2
Psychiatric Disorders
Anxiety | 0 | 8 | 3
Respiratory, Thoracic and Mediastinal Disorders
Pharyngolaryngeal pain | 10 | 3 | 5
Skin and Subcutaneous Tissue Disorders
Rash | 0 | 7 | 2

Commonly-Observed Adverse Reactions in Double-Blind, Placebo-Controlled Clinical Trials - Autistic Disorder

Table 13 lists the adverse reactions reported in 5% or more of RISPERDAL-treated pediatric patients treated for irritability associated with autistic disorder in two 8-week, double-blind, placebo-controlled trials and one 6-week double-blind, placebo-controlled study.

Table 13. Adverse Reactions in ≥5% of RISPERDAL-Treated Pediatric Patients (and greater than placebo) Treated for Irritability Associated with Autistic Disorder in Double-Blind, Placebo-Controlled Trials
 | Percentage of Patients Reporting Reaction
System/Organ Class | RISPERDAL 0.5–4.0 mg/day | Placebo
Adverse Reaction | (N=107) | (N=115)
Gastrointestinal Disorders
Vomiting | 20 | 17
Constipation | 17 | 6
Dry mouth | 10 | 4
Nausea | 8 | 5
Salivary hypersecretion | 7 | 1
General Disorders and Administration Site Conditions
Fatigue | 31 | 9
Pyrexia | 16 | 13
Thirst | 7 | 4
Infections and Infestations
Nasopharyngitis | 19 | 9
Rhinitis | 9 | 7
Upper respiratory tract infection | 8 | 3
Investigations
Weight increased | 8 | 2
Metabolism and Nutrition Disorders
Increased appetite | 44 | 15
Nervous System Disorders
Sedation | 63 | 15
Drooling | 12 | 4
Headache | 12 | 10
Tremor | 8 | 1
Dizziness | 8 | 2
Parkinsonism [Parkinsonism includes musculoskeletal stiffness, extrapyramidal disorder, muscle rigidity, cogwheel rigidity, and muscle tightness.] | 8 | 1
Renal and Urinary Disorders
Enuresis | 16 | 10
Respiratory, Thoracic and Mediastinal Disorders
Cough | 17 | 12
Rhinorrhea | 12 | 10
Nasal congestion | 10 | 4
Skin and Subcutaneous Tissue Disorders
Rash | 8 | 5

Other Adverse Reactions Observed During the Clinical Trial Evaluation of Risperidone

The following additional adverse reactions occurred across all placebo-controlled, active-controlled, and open-label studies of RISPERDAL in adults and pediatric patients.

Blood and Lymphatic System Disorders: anemia, granulocytopenia, neutropenia

Cardiac Disorders: sinus bradycardia, sinus tachycardia, atrioventricular block first degree, bundle branch block left, bundle branch block right, atrioventricular block

Ear and Labyrinth Disorders: ear pain, tinnitus

Endocrine Disorders: hyperprolactinemia

Eye Disorders: ocular hyperemia, eye discharge, conjunctivitis, eye rolling, eyelid edema, eye swelling, eyelid margin crusting, dry eye, lacrimation increased, photophobia, glaucoma, visual acuity reduced

Gastrointestinal Disorders: dysphagia, fecaloma, fecal incontinence, gastritis, lip swelling, cheilitis, aptyalism

General Disorders: edema peripheral, thirst, gait disturbance, influenza-like illness, pitting edema, edema, chills, sluggishness, malaise, chest discomfort, face edema, discomfort, generalized edema, drug withdrawal syndrome, peripheral coldness, feeling abnormal

Immune System Disorders: drug hypersensitivity

Infections and Infestations: pneumonia, influenza, ear infection, viral infection, pharyngitis, tonsillitis, bronchitis, eye infection, localized infection, cystitis, cellulitis, otitis media, onychomycosis, acarodermatitis, bronchopneumonia, respiratory tract infection, tracheobronchitis, otitis media chronic

Investigations: body temperature increased, blood prolactin increased, alanine aminotransferase increased, electrocardiogram abnormal, eosinophil count increased, white blood cell count decreased, blood glucose increased, hemoglobin decreased, hematocrit decreased, body temperature decreased, blood pressure decreased, transaminases increased

Metabolism and Nutrition Disorders: decreased appetite, polydipsia, anorexia

Musculoskeletal and Connective Tissue Disorders: joint stiffness, joint swelling, musculoskeletal chest pain, posture abnormal, myalgia, neck pain, muscular weakness, rhabdomyolysis

Nervous System Disorders: balance disorder, disturbance in attention, dysarthria, unresponsive to stimuli, depressed level of consciousness, movement disorder, transient ischemic attack, coordination abnormal, cerebrovascular accident, speech disorder, syncope, loss of consciousness, hypoesthesia, tardive dyskinesia, dyskinesia, cerebral ischemia, cerebrovascular disorder, neuroleptic malignant syndrome, diabetic coma, head titubation

Psychiatric Disorders: agitation, blunted affect, confusional state, middle insomnia, nervousness, sleep disorder, listlessness, libido decreased, and anorgasmia

Renal and Urinary Disorders: enuresis, dysuria, pollakiuria, urinary incontinence

Reproductive System and Breast Disorders: menstruation irregular, amenorrhea, gynecomastia, galactorrhea, vaginal discharge, menstrual disorder, erectile dysfunction, retrograde ejaculation, ejaculation disorder, sexual dysfunction, breast enlargement

Respiratory, Thoracic, and Mediastinal Disorders: wheezing, pneumonia aspiration, sinus congestion, dysphonia, productive cough, pulmonary congestion, respiratory tract congestion, rales, respiratory disorder, hyperventilation, nasal edema

Skin and Subcutaneous Tissue Disorders: erythema, skin discoloration, skin lesion, pruritus, skin disorder, rash erythematous, rash papular, rash generalized, rash maculopapular, acne, hyperkeratosis, seborrheic dermatitis

Vascular Disorders: hypotension, flushing

Additional Adverse Reactions Reported with RISPERDAL CONSTA

The following is a list of additional adverse reactions that have been reported during the premarketing evaluation of RISPERDAL CONSTA, regardless of frequency of occurrence:

Cardiac Disorders: bradycardia

Ear and Labyrinth Disorders: vertigo

Eye Disorders: blepharospasm

Gastrointestinal Disorders: toothache, tongue spasm

General Disorders and Administration Site Conditions: pain

Infections and Infestations: lower respiratory tract infection, infection, gastroenteritis, subcutaneous abscess

Injury and Poisoning: fall

Investigations: weight decreased, gamma-glutamyltransferase increased, hepatic enzyme increased

Musculoskeletal, Connective Tissue, and Bone Disorders: buttock pain

Nervous System Disorders: convulsion, paresthesia

Psychiatric Disorders: depression

Skin and Subcutaneous Tissue Disorders: eczema

Vascular Disorders: hypertension

Discontinuations Due to Adverse Reactions

Schizophrenia - Adults

Approximately 7% (39/564) of RISPERDAL-treated patients in double-blind, placebo-controlled trials discontinued treatment due to an adverse reaction, compared with 4% (10/225) who were receiving placebo. The adverse reactions associated with discontinuation in 2 or more RISPERDAL-treated patients were:

Table 14. Adverse Reactions Associated With Discontinuation in 2 or More RISPERDAL-Treated Adult Patients in Schizophrenia Trials
 | RISPERDAL
Adverse Reaction | 2–8 mg/day (N=366) | >8–16 mg/day (N=198) | Placebo (N=225)
Dizziness | 1.4% | 1.0% | 0%
Nausea | 1.4% | 0% | 0%
Vomiting | 0.8% | 0% | 0%
Parkinsonism | 0.8% | 0% | 0%
Somnolence | 0.8% | 0% | 0%
Dystonia | 0.5% | 0% | 0%
Agitation | 0.5% | 0% | 0%
Abdominal pain | 0.5% | 0% | 0%
Orthostatic hypotension | 0.3% | 0.5% | 0%
Akathisia | 0.3% | 2.0% | 0%

Discontinuation for extrapyramidal symptoms (including Parkinsonism, akathisia, dystonia, and tardive dyskinesia) was 1% in placebo-treated patients, and 3.4% in active control-treated patients in a double-blind, placebo- and active-controlled trial.

Schizophrenia - Pediatrics

Approximately 7% (7/106), of RISPERDAL-treated patients discontinued treatment due to an adverse reaction in a double-blind, placebo-controlled trial, compared with 4% (2/54) placebo-treated patients. The adverse reactions associated with discontinuation for at least one RISPERDAL-treated patient were dizziness (2%), somnolence (1%), sedation (1%), lethargy (1%), anxiety (1%), balance disorder (1%), hypotension (1%), and palpitation (1%).

Bipolar Mania - Adults

In double-blind, placebo-controlled trials with RISPERDAL as monotherapy, approximately 6% (25/448) of RISPERDAL-treated patients discontinued treatment due to an adverse event, compared with approximately 5% (19/424) of placebo-treated patients. The adverse reactions associated with discontinuation in RISPERDAL-treated patients were:

Table 15. Adverse Reactions Associated With Discontinuation in 2 or More RISPERDAL-Treated Adult Patients in Bipolar Mania Clinical Trials
Adverse Reaction | RISPERDAL 1–6 mg/day (N=448) | Placebo (N=424)
Parkinsonism | 0.4% | 0%
Lethargy | 0.2% | 0%
Dizziness | 0.2% | 0%
Alanine aminotransferase increased | 0.2% | 0.2%
Aspartate aminotransferase increased | 0.2% | 0.2%

Bipolar Mania - Pediatrics

In a double-blind, placebo-controlled trial 12% (13/111) of RISPERDAL-treated patients discontinued due to an adverse reaction, compared with 7% (4/58) of placebo-treated patients. The adverse reactions associated with discontinuation in more than one RISPERDAL-treated pediatric patient were nausea (3%), somnolence (2%), sedation (2%), and vomiting (2%).

Autistic Disorder - Pediatrics

In the two 8-week, placebo-controlled trials in pediatric patients treated for irritability associated with autistic disorder (n=156), one RISPERDAL-treated patient discontinued due to an adverse reaction (Parkinsonism), and one placebo-treated patient discontinued due to an adverse event.

Dose Dependency of Adverse Reactions in Clinical Trials

Extrapyramidal Symptoms

Data from two fixed-dose trials in adults with schizophrenia provided evidence of dose-relatedness for extrapyramidal symptoms associated with RISPERDAL treatment.

Two methods were used to measure extrapyramidal symptoms (EPS) in an 8-week trial comparing 4 fixed doses of RISPERDAL (2, 6, 10, and 16 mg/day), including (1) a Parkinsonism score (mean change from baseline) from the Extrapyramidal Symptom Rating Scale, and (2) incidence of spontaneous complaints of EPS:

Table 16.
Dose Groups | Placebo | RISPERDAL 2 mg | RISPERDAL 6 mg | RISPERDAL 10 mg | RISPERDAL 16 mg
Parkinsonism | 1.2 | 0.9 | 1.8 | 2.4 | 2.6
EPS Incidence | 13% | 17% | 21% | 21% | 35%

Similar methods were used to measure extrapyramidal symptoms (EPS) in an 8-week trial comparing 5 fixed doses of RISPERDAL (1, 4, 8, 12, and 16 mg/day):

Table 17.
Dose Groups | RISPERDAL 1 mg | RISPERDAL 4 mg | RISPERDAL 8 mg | RISPERDAL 12 mg | RISPERDAL 16 mg
Parkinsonism | 0.6 | 1.7 | 2.4 | 2.9 | 4.1
EPS Incidence | 7% | 12% | 17% | 18% | 20%

Dystonia

Class Effect:Symptoms of dystonia, prolonged abnormal contractions of muscle groups, may occur in susceptible individuals during the first few days of treatment. Dystonic symptoms include: spasm of the neck muscles, sometimes progressing to tightness of the throat, swallowing difficulty, difficulty breathing, and/or protrusion of the tongue. While these symptoms can occur at low doses, they occur more frequently and with greater severity with high potency and at higher doses of first generation antipsychotic drugs. An elevated risk of acute dystonia is observed in males and younger age groups.

Other Adverse Reactions

Adverse event data elicited by a checklist for side effects from a large study comparing 5 fixed doses of RISPERDAL (1, 4, 8, 12, and 16 mg/day) were explored for dose-relatedness of adverse events. A Cochran-Armitage Test for trend in these data revealed a positive trend (p<0.05) for the following adverse reactions: somnolence, vision abnormal, dizziness, palpitations, weight increase, erectile dysfunction, ejaculation disorder, sexual function abnormal, fatigue, and skin discoloration.

Changes in Body Weight

Weight gain was observed in short-term, controlled trials and longer-term uncontrolled studies in adult and pediatric patients [see Warnings and Precautions (5.5), Adverse Reactions (6), and Use in Specific Populations (8.4)].

Changes in ECG Parameters

Between-group comparisons for pooled placebo-controlled trials in adults revealed no statistically significant differences between risperidone and placebo in mean changes from baseline in ECG parameters, including QT, QTc, and PR intervals, and heart rate. When all RISPERDAL doses were pooled from randomized controlled trials in several indications, there was a mean increase in heart rate of 1 beat per minute compared to no change for placebo patients. In short-term schizophrenia trials, higher doses of risperidone (8–16 mg/day) were associated with a higher mean increase in heart rate compared to placebo (4–6 beats per minute). In pooled placebo-controlled acute mania trials in adults, there were small decreases in mean heart rate, similar among all treatment groups.

In the two placebo-controlled trials in children and adolescents with autistic disorder (aged 5 – 16 years) mean changes in heart rate were an increase of 8.4 beats per minute in the RISPERDAL groups and 6.5 beats per minute in the placebo group. There were no other notable ECG changes.

In a placebo-controlled acute mania trial in children and adolescents (aged 10 – 17 years), there were no significant changes in ECG parameters, other than the effect of RISPERDAL to transiently increase pulse rate (< 6 beats per minute). In two controlled schizophrenia trials in adolescents (aged 13 – 17 years), there were no clinically meaningful changes in ECG parameters including corrected QT intervals between treatment groups or within treatment groups over time.

6.2 Postmarketing Experience

The following adverse reactions have been identified during postapproval use of risperidone. Because these reactions are reported voluntarily from a population of uncertain size, it is not always possible to reliably estimate their frequency or establish a causal relationship to drug exposure. These adverse reactions include: alopecia, anaphylactic reaction, angioedema, atrial fibrillation, cardiopulmonary arrest, catatonia, diabetic ketoacidosis in patients with impaired glucose metabolism, dysgeusia, hypoglycemia, hypothermia, ileus, inappropriate antidiuretic hormone secretion, intestinal obstruction, jaundice, mania, pancreatitis, pituitary adenoma, precocious puberty, pulmonary embolism, QT prolongation, sleep apnea syndrome, somnambulism, Stevens-Johnson syndrome and toxic epidermal necrolysis (SJS/TEN), sudden death, thrombocytopenia, thrombotic thrombocytopenic purpura, urinary retention, and water intoxication.

Postmarketing cases of extrapyramidal symptoms (dystonia and dyskinesia) have been reported in patients concomitantly taking methylphenidate and risperidone when there was an increase or decrease in dosage, initiation, or discontinuation of either or both medications.

7 DRUG INTERACTIONS

7.1 Pharmacokinetic-related Interactions

The dose of RISPERDAL should be adjusted when used in combination with CYP2D6 enzyme inhibitors (e.g., fluoxetine, and paroxetine) and enzyme inducers (e.g., carbamazepine) [see Table 18and Dosage and Administration (2.5)] . Dose adjustment is not recommended for RISPERDAL when co-administered with ranitidine, cimetidine, amitriptyline, or erythromycin [see Table 18].

Table 18. Summary of Effect of Coadministered Drugs on Exposure to Active Moiety (Risperidone + 9-Hydroxy-Risperidone) in Healthy Subjects or Patients with Schizophrenia
Coadministered Drug | Dosing Schedule |  | Effect on Active Moiety (Risperidone + 9-Hydroxy-Risperidone (Ratio [Change relative to reference]) |  | Risperidone Dose Recommendation
Coadministered Drug | Coadministered Drug | Risperidone | AUC | Cmax | Risperidone Dose Recommendation
Enzyme (CYP2D6) Inhibitors
Fluoxetine | 20 mg/day | 2 or 3 mg twice daily | 1.4 | 1.5 | Re-evaluate dosing. Do not exceed 8 mg/day
Paroxetine | 10 mg/day | 4 mg/day | 1.3 | - | Re-evaluate dosing. Do not exceed 8 mg/day
 | 20 mg/day | 4 mg/day | 1.6 | - | Re-evaluate dosing. Do not exceed 8 mg/day
 | 40 mg/day | 4 mg/day | 1.8 | - | Re-evaluate dosing. Do not exceed 8 mg/day
Enzyme (CYP3A/PgP inducers) Inducers
Carbamazepine | 573 ± 168 mg/day | 3 mg twice daily | 0.51 | 0.55 | Titrate dose upwards. Do not exceed twice the patient's usual dose
Enzyme (CYP3A) Inhibitors
Ranitidine | 150 mg twice daily | 1 mg single dose | 1.2 | 1.4 | Dose adjustment not needed
Cimetidine | 400 mg twice daily | 1 mg single dose | 1.1 | 1.3 | Dose adjustment not needed
Erythromycin | 500 mg four times daily | 1 mg single dose | 1.1 | 0.94 | Dose adjustment not needed
Other Drugs
Amitriptyline | 50 mg twice daily | 3 mg twice daily | 1.2 | 1.1 | Dose adjustment not needed

Effect of Risperidone on Other Drugs

Lithium

Repeated oral doses of RISPERDAL (3 mg twice daily) did not affect the exposure (AUC) or peak plasma concentrations (Cmax) of lithium (n=13). Dose adjustment for lithium is not recommended.

Valproate

Repeated oral doses of RISPERDAL (4 mg once daily) did not affect the pre-dose or average plasma concentrations and exposure (AUC) of valproate (1000 mg/day in three divided doses) compared to placebo (n=21). However, there was a 20% increase in valproate peak plasma concentration (Cmax) after concomitant administration of RISPERDAL. Dose adjustment for valproate is not recommended.

Digoxin

RISPERDAL (0.25 mg twice daily) did not show a clinically relevant effect on the pharmacokinetics of digoxin. Dose adjustment for digoxin is not recommended.

7.2 Pharmacodynamic-related Interactions

Centrally Acting Drugs and Alcohol

Given the primary CNS effects of risperidone, caution should be used when RISPERDAL is taken in combination with other centrally acting drugs and alcohol.

Drugs with Hypotensive Effects

Because of its potential for inducing hypotension, RISPERDAL may enhance the hypotensive effects of other therapeutic agents with this potential.

Levodopa and Dopamine Agonists

RISPERDAL may antagonize the effects of levodopa and dopamine agonists.

Methylphenidate

Concomitant use with methylphenidate, when there is change in dosage of either medication, may increase the risk of extrapyramidal symptoms (EPS). Monitor for symptoms of EPS with concomitant use of RISPERDAL and methylphenidate [see Adverse Reactions (6.2)] .

Clozapine

Chronic administration of clozapine with RISPERDAL may decrease the clearance of risperidone.

8 USE IN SPECIFIC POPULATIONS

8.1 Pregnancy

Pregnancy Exposure Registry

There is a pregnancy exposure registry that monitors pregnancy outcomes in women exposed to atypical antipsychotics, including RISPERDAL, during pregnancy. Healthcare providers are encouraged to register patients by contacting the National Pregnancy Registry for Atypical Antipsychotics at 1-866-961-2388 or online at http://womensmentalhealth.org/clinical-and-research-programs/pregnancyregistry/.

Risk Summary

Neonates exposed to antipsychotic drugs during the third trimester of pregnancy are at risk for extrapyramidal and/or withdrawal symptoms following delivery (see Clinical Considerations) . Overall, available data from published epidemiologic studies of pregnant women exposed to risperidone have not established a drug-associated risk of major birth defects, miscarriage, or adverse maternal or fetal outcomes (see Data). There are risks to the mother associated with untreated schizophrenia or bipolar I disorder and with exposure to antipsychotics, including RISPERDAL, during pregnancy (see Clinical Considerations) .

Oral administration of risperidone to pregnant mice caused cleft palate at doses 3 to 4 times the maximum recommended human dose (MRHD) with maternal toxicity observed at 4-times MRHD based on mg/m^2body surface area. Risperidone was not teratogenic in rats or rabbits at doses up to 6-times the MRHD based on mg/m^2body surface area. Increased stillbirths and decreased birth weight occurred after oral risperidone administration to pregnant rats at 1.5-times the MRHD based on mg/m^2body surface area. Learning was impaired in offspring of rats when the dams were dosed at 0.6-times the MRHD and offspring mortality increased at doses 0.1 to 3 times the MRHD based on mg/m^2body surface area.

The estimated background risk of major birth defects and miscarriage for the indicated population is unknown. All pregnancies have a background risk of birth defect, loss, or other adverse outcomes. In the U.S. general population, the estimated background risk of major birth defects and miscarriage in clinically recognized pregnancies is 2–4% and 15–20%, respectively.

Clinical Considerations

Disease-associated maternal and/or embryo/fetal risk

There is a risk to the mother from untreated schizophrenia or bipolar I disorder, including increased risk of relapse, hospitalization, and suicide. Schizophrenia and bipolar I disorder are associated with increased adverse perinatal outcomes, including preterm birth. It is not known if this is a direct result of the illness or other comorbid factors.

Fetal/Neonatal Adverse Reactions

Extrapyramidal and/or withdrawal symptoms, including agitation, hypertonia, hypotonia, tremor, somnolence, respiratory distress, and feeding disorder have been reported in neonates who were exposed to antipsychotic drugs, including RISPERDAL, during the third trimester of pregnancy. These symptoms have varied in severity. Monitor neonates for extrapyramidal and/or withdrawal symptoms and manage symptoms appropriately. Some neonates recovered within hours or days without specific treatment; others required prolonged hospitalization.

Data

Human Data

Published data from observational studies, birth registries, and case reports on the use of atypical antipsychotics during pregnancy do not report a clear association with antipsychotics and major birth defects. A prospective observational study including 6 women treated with risperidone demonstrated placental passage of risperidone. A retrospective cohort study from a Medicaid database of 9258 women exposed to antipsychotics during pregnancy did not indicate an overall increased risk for major birth defects. There was a small increase in the risk of major birth defects (RR=1.26, 95% CI 1.02–1.56) and of cardiac malformations (RR=1.26, 95% CI 0.88–1.81) in a subgroup of 1566 women exposed to risperidone during the first trimester of pregnancy; however, there is no mechanism of action to explain the difference in malformation rates.

Animal Data

Oral administration of risperidone to pregnant mice during organogenesis caused cleft palate at 10 mg/kg/day which is 3 times the MRHD of 16 mg/day based on mg/m^2body surface area: maternal toxicity occurred at 4 times the MRHD. Risperidone was not teratogenic when administered orally to rats at 0.6 to 10 mg/kg/day and rabbits at 0.3 to 5 mg/kg/day, which are up to 6 times the MRHD of 16 mg/day risperidone based on mg/m^2body surface area. Learning was impaired in offspring of rats dosed orally throughout pregnancy at 1 mg/kg/day which is 0.6 times the MRHD and neuronal cell death increased in fetal brains of offspring of rats dosed during pregnancy at 1 and 2 mg/kg/day which are 0.6 and 1.2 times the MRHD based on mg/m^2body surface area; postnatal development and growth of the offspring were also delayed.

Rat offspring mortality increased during the first 4 days of lactation when pregnant rats were dosed throughout gestation at 0.16 to 5 mg/kg/day which are 0.1 to 3 times the MRHD of 16 mg/day based on mg/m^2body surface area. It is not known whether these deaths were due to a direct effect on the fetuses or pups or to effects on the dams; a no-effect dose could not be determined. The rate of stillbirths was increased at 2.5 mg/kg or 1.5 times the MRHD based on mg/m^2body surface area.

In a rat cross-fostering study the number of live offspring was decreased, the number of stillbirths increased, and the birth weight was decreased in offspring of drug-treated pregnant rats. In addition, the number of deaths increased by Day 1 among offspring of drug-treated pregnant rats, regardless of whether or not the offspring were cross-fostered. Risperidone also appeared to impair maternal behavior in that offspring body weight gain and survival (from Day 1 to 4 of lactation) were reduced in offspring born to control but reared by drug-treated dams. All of these effects occurred at 5 mg/kg which is 3 times the MRHD based on mg/m^2and the only dose tested in the study.

8.2 Lactation

Risk Summary

Limited data from published literature reports the presence of risperidone and its metabolite, 9-hydroxyrisperidone, in human breast milk at relative infant dose ranging between 2.3% and 4.7% of the maternal weight-adjusted dosage. There are reports of sedation, failure to thrive, jitteriness, and extrapyramidal symptoms (tremors and abnormal muscle movements) in breastfed infants exposed to risperidone (see Clinical Considerations). There is no information on the effects of risperidone on milk production. The developmental and health benefits of breastfeeding should be considered along with the mother's clinical need for RISPERDAL and any potential adverse effects on the breastfed child from RISPERDAL or from the mother's underlying condition.

Clinical Considerations

Infants exposed to RISPERDAL through breastmilk should be monitored for excess sedation, failure to thrive, jitteriness, and extrapyramidal symptoms (tremors and abnormal muscle movements).

8.3 Females and Males of Reproductive Potential

Infertility

Females

Based on the pharmacologic action of risperidone (D2receptor antagonism), treatment with RISPERDAL may result in an increase in serum prolactin levels ,which may lead to a reversible reduction in fertility in females of reproductive potential [see Warnings and Precautions (5.6)].

8.4 Pediatric Use

Approved Pediatric Indications

Schizophrenia

The efficacy and safety of RISPERDAL in the treatment of schizophrenia were demonstrated in 417 adolescents, aged 13 to 17 years, in two short-term (6 and 8 weeks, respectively) double-blind controlled trials [see Indications and Usage (1.1), Adverse Reactions (6.1), and Clinical Studies (14.1)]. Additional safety and efficacy information was also assessed in one long-term (6-month) open-label extension study in 284 of these adolescent patients with schizophrenia.

Safety and effectiveness of RISPERDAL in children less than 13 years of age with schizophrenia have not been established.

Bipolar I Disorder

The efficacy and safety of RISPERDAL in the short-term treatment of acute manic or mixed episodes associated with Bipolar I Disorder in 169 children and adolescent patients, aged 10 to 17 years, were demonstrated in one double-blind, placebo-controlled, 3-week trial [see Indications and Usage (1.2), Adverse Reactions (6.1), and Clinical Studies (14.2)] .

Safety and effectiveness of RISPERDAL in children less than 10 years of age with bipolar disorder have not been established.

Autistic Disorder

The efficacy and safety of RISPERDAL in the treatment of irritability associated with autistic disorder were established in two 8-week, double-blind, placebo-controlled trials in 156 children and adolescent patients, aged 5 to 16 years [see Indications and Usage (1.3), Adverse Reactions (6.1) and Clinical Studies (14.4)]. Additional safety information was also assessed in a long-term study in patients with autistic disorder, or in short- and long-term studies in more than 1200 pediatric patients with psychiatric disorders other than autistic disorder, schizophrenia, or bipolar mania who were of similar age and weight, and who received similar dosages of RISPERDAL as patients treated for irritability associated with autistic disorder.

A third study was a 6-week, multicenter, randomized, double-blind, placebo-controlled, fixed-dose study to evaluate the efficacy and safety of a lower than recommended dose of risperidone in subjects 5 to 17 years of age with autistic disorder and associated irritability, and related behavioral symptoms. There were two weight-based, fixed doses of risperidone (high-dose and low-dose). The high dose was 1.25 mg per day for patients weighing 20 to < 45 kg, and it was 1.75 mg per day for patients weighing ≥ 45 kg. The low dose was 0.125 mg per day for patients for patients weighing 20 to < 45 kg, and it was 0.175 mg per day for patients weighing ≥ 45 kg. The study demonstrated the efficacy of high-dose risperidone, but it did not demonstrate efficacy for low-dose risperidone.

Adverse Reactions in Pediatric Patients

Tardive Dyskinesia

In clinical trials in 1885 children and adolescents treated with RISPERDAL, 2 (0.1%) patients were reported to have tardive dyskinesia, which resolved on discontinuation of RISPERDAL treatment [see also Warnings and Precautions (5.4)] .

Weight Gain

Weight gain has been observed in children and adolescents during treatment with RISPERDAL. Clinical monitoring of weight is recommended during treatment.

Data derive from short-term placebo-controlled trials and longer-term uncontrolled studies in pediatric patients (ages 5 to 17 years) with schizophrenia, bipolar disorder, autistic disorder, or other psychiatric disorders. In the short-term trials (3 to 8 weeks), the mean weight gain for RISPERDAL-treated patients was 2 kg, compared to 0.6 kg for placebo-treated patients. In these trials, approximately 33% of the RISPERDAL group had weight gain ≥7%, compared to 7% in the placebo group. In longer-term, uncontrolled, open-label pediatric studies, the mean weight gain was 5.5 kg at Week 24 and 8 kg at Week 48 [see Warnings and Precautions (5.5)and Adverse Reactions (6.1)].

Somnolence

Somnolence was frequently observed in placebo-controlled clinical trials of pediatric patients with autistic disorder. Most cases were mild or moderate in severity. These events were most often of early onset with peak incidence occurring during the first two weeks of treatment, and transient with a median duration of 16 days. Somnolence was the most commonly observed adverse reaction in the clinical trial of bipolar disorder in children and adolescents, as well as in the schizophrenia trials in adolescents. As was seen in the autistic disorder trials, these adverse reactions were most often of early onset and transient in duration [see Adverse Reactions (6.1and 6.2)] . Patients experiencing persistent somnolence may benefit from a change in dosing regimen [see Dosage and Administration (2.1, 2.2, and 2.3)] .

Hyperprolactinemia

RISPERDAL has been shown to elevate prolactin levels in children and adolescents as well as in adults [see Warnings and Precautions (5.6)] . In double-blind, placebo-controlled studies of up to 8 weeks duration in children and adolescents (aged 5 to 17 years) with autistic disorder or psychiatric disorders other than autistic disorder, schizophrenia, or bipolar mania, 49% of patients who received RISPERDAL had elevated prolactin levels compared to 2% of patients who received placebo. Similarly, in placebo-controlled trials in children and adolescents (aged 10 to 17 years) with bipolar disorder, or adolescents (aged 13 to 17 years) with schizophrenia, 82–87% of patients who received RISPERDAL had elevated levels of prolactin compared to 3–7% of patients on placebo. Increases were dose-dependent and generally greater in females than in males across indications.

In clinical trials in 1885 children and adolescents, galactorrhea was reported in 0.8% of RISPERDAL-treated patients and gynecomastia was reported in 2.3% of RISPERDAL-treated patients.

Growth and Sexual Maturation

The long-term effects of RISPERDAL on growth and sexual maturation have not been fully evaluated in children and adolescents.

Juvenile Animal Studies

Juvenile dogs were treated with oral risperidone from weeks 10 to 50 of age (equivalent to the period of childhood through adolescence in humans), at doses of 0.31, 1.25, or 5 mg/kg/day, which are 1.2, 3.4, and 13.5 times the MRHD of 6 mg/day for children, based on mg/m^2body surface area. Bone length and density were decreased with a no-effect dose of 0.31 mg/kg/day; this dose produced plasma AUC of risperidone plus its active metabolite paliperidone (9-hydroxy-risperidone) that were similar to those in children and adolescents receiving the MRHD of 6 mg/day. In addition, sexual maturation was delayed at all doses in both males and females. The above effects showed little or no reversibility in females after a 12 week drug-free recovery period.

Juvenile rats, treated with oral risperidone from days 12 to 50 of age (equivalent to the period of infancy through adolescence in humans) showed impaired learning and memory performance (reversible only in females), with a no-effect dose of 0.63 mg/kg/day which is 0.5 times the MRHD of 6 mg/day for children, based on mg/m^2body surface area. This dose produced plasma AUC of risperidone plus paliperidone about half the exposure observed in humans at the MRHD. No other consistent effects on neurobehavioral or reproductive development were seen up to the highest tested dose of 1.25 mg/kg/day which is 1 time the MRHD and produced plasma AUC of risperidone plus paliperidone that were about two thirds of those observed in humans at the MRHD of 6 mg/day for children.

8.5 Geriatric Use

Clinical studies of RISPERDAL in the treatment of schizophrenia did not include sufficient numbers of patients aged 65 and over to determine whether or not they respond differently than younger patients. Other reported clinical experience has not identified differences in responses between elderly and younger patients. In general, a lower starting dose is recommended for an elderly patient, reflecting a decreased pharmacokinetic clearance in the elderly, as well as a greater frequency of decreased hepatic, renal, or cardiac function, and of concomitant disease or other drug therapy [see Clinical Pharmacology (12.3) and Dosage and Administration (2.4, 2.5)] . While elderly patients exhibit a greater tendency to orthostatic hypotension, its risk in the elderly may be minimized by limiting the initial dose to 0.5 mg twice daily followed by careful titration [see Warnings and Precautions (5.7)] . Monitoring of orthostatic vital signs should be considered in patients for whom this is of concern.

This drug is substantially excreted by the kidneys, and the risk of toxic reactions to this drug may be greater in patients with impaired renal function. Because elderly patients are more likely to have decreased renal function, care should be taken in dose selection, and it may be useful to monitor renal function [see Dosage and Administration (2.4)] .

8.6 Renal Impairment

In patients with moderate to severe (Clcr 59 to 15 mL/min) renal disease, clearance of the sum of risperidone and its active metabolite decreased by 60%, compared to young healthy subjects. RISPERDAL doses should be reduced in patients with renal disease [see Dosage and Administration (2.4)] .

8.7 Hepatic Impairment

While the pharmacokinetics of risperidone in subjects with liver disease were comparable to those in young healthy subjects, the mean free fraction of risperidone in plasma was increased by about 35% because of the diminished concentration of both albumin and α1-acid glycoprotein. RISPERDAL doses should be reduced in patients with liver disease [see Dosage and Administration (2.4)] .

8.8 Patients with Parkinson's Disease or Lewy Body Dementia

Patients with Parkinson's Disease or Dementia with Lewy Bodies can experience increased sensitivity to RISPERDAL. Manifestations can include confusion, obtundation, postural instability with frequent falls, extrapyramidal symptoms, and clinical features consistent with neuroleptic malignant syndrome.

9 DRUG ABUSE AND DEPENDENCE

9.1 Controlled Substance

RISPERDAL (risperidone) is not a controlled substance.

9.2 Abuse

RISPERDAL has not been systematically studied in animals or humans for its potential for abuse. While the clinical trials did not reveal any tendency for any drug-seeking behavior, these observations were not systematic and it is not possible to predict on the basis of this limited experience the extent to which a CNS-active drug will be misused, diverted, and/or abused once marketed. Consequently, patients should be evaluated carefully for a history of drug abuse, and such patients should be observed closely for signs of RISPERDAL misuse or abuse (e.g., development of tolerance, increases in dose, drug-seeking behavior).

9.3 Dependence

RISPERDAL has not been systematically studied in animals or humans for its potential for tolerance or physical dependence.

10 OVERDOSAGE

10.1 Human Experience

Premarketing experience included eight reports of acute RISPERDAL overdosage with estimated doses ranging from 20 to 300 mg and no fatalities. In general, reported signs and symptoms were those resulting from an exaggeration of the drug's known pharmacological effects, i.e., drowsiness and sedation, tachycardia and hypotension, and extrapyramidal symptoms. One case, involving an estimated overdose of 240 mg, was associated with hyponatremia, hypokalemia, prolonged QT, and widened QRS. Another case, involving an estimated overdose of 36 mg, was associated with a seizure.

Postmarketing experience includes reports of acute RISPERDAL overdosage, with estimated doses of up to 360 mg. In general, the most frequently reported signs and symptoms are those resulting from an exaggeration of the drug's known pharmacological effects, i.e., drowsiness, sedation, tachycardia, hypotension, and extrapyramidal symptoms. Other adverse reactions reported since market introduction related to RISPERDAL overdose include prolonged QT interval and convulsions. Torsade de pointes has been reported in association with combined overdose of RISPERDAL and paroxetine.

10.2 Management of Overdosage

For the most up to date information on the management of RISPERDAL overdosage, contact a certified poison control center (1-800-222-1222 or www.poison.org). Provide supportive care including close medical supervision and monitoring. Treatment should consist of general measures employed in the management of overdosage with any drug. Consider the possibility of multiple drug overdosage. Ensure an adequate airway, oxygenation, and ventilation. Monitor cardiac rhythm and vital signs. Use supportive and symptomatic measures. There is no specific antidote to RISPERDAL.

11 DESCRIPTION

RISPERDAL®contains risperidone, an atypical antipsychotic belonging to the chemical class of benzisoxazole derivatives. The chemical designation is 3-[2-[4-(6-fluoro-1,2-benzisoxazol-3-yl)-1-piperidinyl]ethyl]-6,7,8,9-tetrahydro-2-methyl-4H-pyrido[1,2-a]pyrimidin-4-one. Its molecular formula is C23H27FN4O2and its molecular weight is 410.49. The structural formula is:

Risperidone is a white to slightly beige powder. It is practically insoluble in water, freely soluble in methylene chloride, and soluble in methanol and 0.1 NHCl.

RISPERDAL®Tablets are for oral administration and available in 0.5 mg (red-brown), 1 mg (white), 2 mg (orange), 3 mg (yellow), and 4 mg (green) strengths. RISPERDAL tablets contain the following inactive ingredients: colloidal silicon dioxide, hypromellose, lactose, magnesium stearate, microcrystalline cellulose, propylene glycol, sodium lauryl sulfate, and starch (corn). The 0.5 mg, 2 mg, 3 mg, and 4 mg tablets also contain talc and titanium dioxide. The 0.5 mg tablets contain red iron oxide; the 2 mg tablets contain FD&C Yellow No. 6 Aluminum Lake; the 3 mg and 4 mg tablets contain D&C Yellow No. 10; the 4 mg tablets contain FD&C Blue No. 2 Aluminum Lake.

RISPERDAL is also available as a 1 mg/mL oral solution. RISPERDAL®Oral Solution contains the following inactive ingredients: tartaric acid, benzoic acid, sodium hydroxide, and purified water.

RISPERDAL®M-TAB®Orally Disintegrating Tablets are available in 0.5 mg (light coral), 1 mg (light coral), 2 mg (coral), 3 mg (coral), and 4 mg (coral) strengths. RISPERDAL M-TAB Orally Disintegrating Tablets contain the following inactive ingredients: Amberlite®resin, gelatin, mannitol, glycine, simethicone, carbomer, sodium hydroxide, aspartame, red ferric oxide, and peppermint oil. In addition, the 2 mg, 3 mg, and 4 mg RISPERDAL M-TAB Orally Disintegrating Tablets contain xanthan gum.

12 CLINICAL PHARMACOLOGY

12.1 Mechanism of Action

The mechanism of action of risperidone in schizophrenia is unclear. The drug's therapeutic activity in schizophrenia could be mediated through a combination of dopamine Type 2 (D2) and serotonin Type 2 (5HT2) receptor antagonism. The clinical effect from risperidone results from the combined concentrations of risperidone and its major metabolite, 9-hydroxyrisperidone (paliperidone) [see Clinical Pharmacology (12.3)] . Antagonism at receptors other than D2and 5HT2may explain some of the other effects of risperidone [see Clinical Pharmacology (12.1)] .

12.2 Pharmacodynamics

Risperidone is a monoaminergic antagonist with high affinity (Ki of 0.12 to 7.3 nM) for the serotonin Type 2 (5HT2), dopamine Type 2 (D2), α1and α2adrenergic, and H1histaminergic receptors. Risperidone showed low to moderate affinity (Ki of 47 to 253 nM) for the serotonin 5HT1C, 5HT1D, and 5HT1Areceptors, weak affinity (Ki of 620 to 800 nM) for the dopamine D1and haloperidol-sensitive sigma site, and no affinity (when tested at concentrations >10^-5M) for cholinergic muscarinic or β1and β2adrenergic receptors.

12.3 Pharmacokinetics

Absorption

Risperidone is well absorbed. The absolute oral bioavailability of risperidone is 70% (CV=25%). The relative oral bioavailability of risperidone from a tablet is 94% (CV=10%) when compared to a solution.

Pharmacokinetic studies showed that RISPERDAL M-TAB Orally Disintegrating Tablets and RISPERDAL Oral Solution are bioequivalent to RISPERDAL Tablets.

Plasma concentrations of risperidone, its major metabolite, 9-hydroxyrisperidone, and risperidone plus 9-hydroxyrisperidone are dose proportional over the dosing range of 1 to 16 mg daily (0.5 to 8 mg twice daily). Following oral administration of solution or tablet, mean peak plasma concentrations of risperidone occurred at about 1 hour. Peak concentrations of 9-hydroxyrisperidone occurred at about 3 hours in extensive metabolizers, and 17 hours in poor metabolizers. Steady-state concentrations of risperidone are reached in 1 day in extensive metabolizers and would be expected to reach steady-state in about 5 days in poor metabolizers. Steady-state concentrations of 9-hydroxyrisperidone are reached in 5–6 days (measured in extensive metabolizers).

Food Effect

Food does not affect either the rate or extent of absorption of risperidone. Thus, RISPERDAL can be given with or without meals.

Distribution

Risperidone is rapidly distributed. The volume of distribution is 1–2 L/kg. In plasma, risperidone is bound to albumin and α1-acid glycoprotein. The plasma protein binding of risperidone is approximately 90%, and that of its major metabolite, 9-hydroxyrisperidone, is 77%. Neither risperidone nor 9-hydroxyrisperidone displaces each other from plasma binding sites. High therapeutic concentrations of sulfamethazine (100 mcg/mL), warfarin (10 mcg/mL), and carbamazepine (10mcg/mL) caused only a slight increase in the free fraction of risperidone at 10 ng/mL and 9-hydroxyrisperidone at 50 ng/mL, changes of unknown clinical significance.

Elimination

Metabolism

Risperidone is extensively metabolized in the liver. The main metabolic pathway is through hydroxylation of risperidone to 9-hydroxyrisperidone by the enzyme, CYP 2D6. A minor metabolic pathway is through N-dealkylation. The main metabolite, 9-hydroxyrisperidone, has similar pharmacological activity as risperidone. Consequently, the clinical effect of the drug results from the combined concentrations of risperidone plus 9-hydroxyrisperidone.

CYP 2D6, also called debrisoquin hydroxylase, is the enzyme responsible for metabolism of many neuroleptics, antidepressants, antiarrhythmics, and other drugs. CYP 2D6 is subject to genetic polymorphism (about 6%–8% of Caucasians, and a very low percentage of Asians, have little or no activity and are "poor metabolizers") and to inhibition by a variety of substrates and some non-substrates, notably quinidine. Extensive CYP 2D6 metabolizers convert risperidone rapidly into 9-hydroxyrisperidone, whereas poor CYP 2D6 metabolizers convert it much more slowly. Although extensive metabolizers have lower risperidone and higher 9-hydroxyrisperidone concentrations than poor metabolizers, the pharmacokinetics of risperidone and 9-hydroxyrisperidone combined, after single and multiple doses, are similar in extensive and poor metabolizers.

Excretion

Risperidone and its metabolites are eliminated via the urine and, to a much lesser extent, via the feces. As illustrated by a mass balance study of a single 1 mg oral dose of^14C-risperidone administered as solution to three healthy male volunteers, total recovery of radioactivity at 1 week was 84%, including 70% in the urine and 14% in the feces.

The apparent half-life of risperidone was 3 hours (CV=30%) in extensive metabolizers and 20 hours (CV=40%) in poor metabolizers. The apparent half-life of 9-hydroxyrisperidone was about 21 hours (CV=20%) in extensive metabolizers and 30 hours (CV=25%) in poor metabolizers. The pharmacokinetics of risperidone and 9-hydroxyrisperidone combined, after single and multiple doses, were similar in extensive and poor metabolizers, with an overall mean elimination half-life of about 20 hours.

Drug Interaction Studies

Risperidone could be subject to two kinds of drug-drug interactions. First, inhibitors of CYP 2D6 interfere with conversion of risperidone to 9-hydroxyrisperidone [see Drug Interactions (7)] . This occurs with quinidine, giving essentially all recipients a risperidone pharmacokinetic profile typical of poor metabolizers. The therapeutic benefits and adverse effects of risperidone in patients receiving quinidine have not been evaluated, but observations in a modest number (n≅70) of poor metabolizers given RISPERDAL do not suggest important differences between poor and extensive metabolizers. Second, co-administration of known enzyme inducers (e.g., carbamazepine, phenytoin, rifampin, and phenobarbital) with RISPERDAL may cause a decrease in the combined plasma concentrations of risperidone and 9-hydroxyrisperidone [see Drug Interactions (7)] . It would also be possible for risperidone to interfere with metabolism of other drugs metabolized by CYP 2D6. Relatively weak binding of risperidone to the enzyme suggests this is unlikely [see Drug Interactions (7)] .

In vitrostudies indicate that risperidone is a relatively weak inhibitor of CYP 2D6. Therefore, RISPERDAL is not expected to substantially inhibit the clearance of drugs that are metabolized by this enzymatic pathway. In drug interaction studies, RISPERDAL did not significantly affect the pharmacokinetics of donepezil and galantamine, which are metabolized by CYP 2D6.

In vitrostudies demonstrated that drugs metabolized by other CYP isozymes, including 1A1, 1A2, 2C9, 2C19, and 3A4, are only weak inhibitors of risperidone metabolism.

Specific Populations

Renal and Hepatic Impairment

[See Use in Specific Populations (8.6and 8.7)].

Elderly

In healthy elderly subjects, renal clearance of both risperidone and 9-hydroxyrisperidone was decreased, and elimination half-lives were prolonged compared to young healthy subjects. Dosing should be modified accordingly in the elderly patients [see Use in Specific Populations (8.5)] .

Pediatric

The pharmacokinetics of risperidone and 9-hydroxyrisperidone in children were similar to those in adults after correcting for the difference in body weight.

Race and Gender Effects

No specific pharmacokinetic study was conducted to investigate race and gender effects, but a population pharmacokinetic analysis did not identify important differences in the disposition of risperidone due to gender (whether corrected for body weight or not) or race.

13 NONCLINICAL TOXICOLOGY

13.1 Carcinogenesis, Mutagenesis, Impairment of Fertility

Carcinogenesis

Risperidone was administered in the diet at doses of 0.63, 2.5, and 10 mg/kg for 18 months to mice and for 25 months to rats. These doses are equivalent to approximately 0.2, 0.75, and 3 times (mice) and 0.4, 1.5, and 6 times (rats) the MRHD of 16 mg/day, based on mg/m^2body surface area. A maximum tolerated dose was not achieved in male mice. There were statistically significant increases in pituitary gland adenomas, endocrine pancreas adenomas, and mammary gland adenocarcinomas. The table below summarizes the multiples of the human dose on a mg/m^2(mg/kg) basis at which these tumors occurred.

 |  |  | Multiples of Maximum Human Dose in mg/m^2(mg/kg)
Tumor Type | Species | Sex | Lowest Effect Level | Highest No-Effect Level
Pituitary adenomas | mouse | Female | 0.75 (9.4) | 0.2 (2.4)
Endocrine pancreas adenomas | rat | Male | 1.5 (9.4) | 0.4 (2.4)
Mammary gland adenocarcinomas | mouse | Female | 0.2 (2.4) | none
 | rat | Female | 0.4 (2.4) | none
 | rat | Male | 6.0 (37.5) | 1.5 (9.4)
Mammary gland neoplasm, Total | rat | Male | 1.5 (9.4) | 0.4 (2.4)

Antipsychotic drugs have been shown to chronically elevate prolactin levels in rodents. Serum prolactin levels were not measured during the risperidone carcinogenicity studies; however, measurements during subchronic toxicity studies showed that risperidone elevated serum prolactin levels 5–6 fold in mice and rats at the same doses used in the carcinogenicity studies. An increase in mammary, pituitary, and endocrine pancreas neoplasms has been found in rodents after chronic administration of other antipsychotic drugs and is considered to be prolactin-mediated. The relevance for human risk of the findings of prolactin-mediated endocrine tumors in rodents is unclear [see Warnings and Precautions (5.6)] .

Mutagenesis

No evidence of mutagenic or clastogenic potential for risperidone was found in the in vitrotests of Ames gene mutation, the mouse lymphoma assay, rat hepatocyte DNA-repair assay, the chromosomal aberration test in human lymphocytes, Chinese hamster ovary cells, or in the in vivooral micronucleus test in mice and the sex-linked recessive lethal test in Drosophila.

Impairment of Fertility

Oral risperidone (0.16 to 5 mg/kg) impaired mating, but not fertility, in rat reproductive studies at doses 0.1 to 3 times the MRHD of 16 mg/day based on mg/m^2body surface area. The effect appeared to be in females, since impaired mating behavior was not noted in the male fertility study. In a subchronic study in Beagle dogs in which risperidone was administered orally at doses of 0.31 to 5 mg/kg, sperm motility and concentration were decreased at doses 0.6 to 10 times the MRHD based on mg/m^2body surface area. Dose-related decreases were also noted in serum testosterone at the same doses. Serum testosterone and sperm parameters partially recovered, but remained decreased after treatment was discontinued. A no-effect dose could not be determined in either rat or dog.

14 CLINICAL STUDIES

14.1 Schizophrenia

Adults

Short-Term Efficacy

The efficacy of RISPERDAL in the treatment of schizophrenia was established in four short-term (4- to 8-week) controlled trials of psychotic inpatients who met DSM-III-R criteria for schizophrenia.

Several instruments were used for assessing psychiatric signs and symptoms in these studies, among them the Brief Psychiatric Rating Scale (BPRS), a multi-item inventory of general psychopathology traditionally used to evaluate the effects of drug treatment in schizophrenia. The BPRS psychosis cluster (conceptual disorganization, hallucinatory behavior, suspiciousness, and unusual thought content) is considered a particularly useful subset for assessing actively psychotic schizophrenic patients. A second traditional assessment, the Clinical Global Impression (CGI), reflects the impression of a skilled observer, fully familiar with the manifestations of schizophrenia, about the overall clinical state of the patient. In addition, the Positive and Negative Syndrome Scale (PANSS) and the Scale for Assessing Negative Symptoms (SANS) were employed.

The results of the trials follow:

- In a 6-week, placebo-controlled trial (n=160) involving titration of RISPERDAL in doses up to 10 mg/day (twice-daily schedule), RISPERDAL was generally superior to placebo on the BPRS total score, on the BPRS psychosis cluster, and marginally superior to placebo on the SANS.
- In an 8-week, placebo-controlled trial (n=513) involving 4 fixed doses of RISPERDAL (2 mg/day, 6 mg/day, 10 mg/day, and 16 mg/day, on a twice-daily schedule), all 4 RISPERDAL groups were generally superior to placebo on the BPRS total score, BPRS psychosis cluster, and CGI severity score; the 3 highest RISPERDAL dose groups were generally superior to placebo on the PANSS negative subscale. The most consistently positive responses on all measures were seen for the 6 mg dose group, and there was no suggestion of increased benefit from larger doses.
- In an 8-week, dose comparison trial (n=1356) involving 5 fixed doses of RISPERDAL (1 mg/day, 4 mg/day, 8 mg/day, 12 mg/day, and 16 mg/day, on a twice-daily schedule), the four highest RISPERDAL dose groups were generally superior to the 1 mg RISPERDAL dose group on BPRS total score, BPRS psychosis cluster, and CGI severity score. None of the dose groups were superior to the 1 mg group on the PANSS negative subscale. The most consistently positive responses were seen for the 4 mg dose group.
- In a 4-week, placebo-controlled dose comparison trial (n=246) involving 2 fixed doses of RISPERDAL (4 and 8 mg/day on a once-daily schedule), both RISPERDAL dose groups were generally superior to placebo on several PANSS measures, including a response measure (>20% reduction in PANSS total score), PANSS total score, and the BPRS psychosis cluster (derived from PANSS). The results were generally stronger for the 8 mg than for the 4 mg dose group.

Long-Term Efficacy

In a longer-term trial, 365 adult outpatients predominantly meeting DSM-IV criteria for schizophrenia and who had been clinically stable for at least 4 weeks on an antipsychotic medication were randomized to RISPERDAL (2–8 mg/day) or to an active comparator, for 1 to 2 years of observation for relapse. Patients receiving RISPERDAL experienced a significantly longer time to relapse over this time period compared to those receiving the active comparator.

Pediatrics

The efficacy of RISPERDAL in the treatment of schizophrenia in adolescents aged 13–17 years was demonstrated in two short-term (6 and 8 weeks), double-blind controlled trials. All patients met DSM-IV diagnostic criteria for schizophrenia and were experiencing an acute episode at time of enrollment. In the first trial (study #1), patients were randomized into one of three treatment groups: RISPERDAL 1–3 mg/day (n=55, mean modal dose = 2.6 mg), RISPERDAL 4–6 mg/day (n=51, mean modal dose = 5.3 mg), or placebo (n=54). In the second trial (study #2), patients were randomized to either RISPERDAL 0.15–0.6 mg/day (n=132, mean modal dose = 0.5 mg) or RISPERDAL 1.5–6 mg/day (n=125, mean modal dose = 4 mg). In all cases, study medication was initiated at 0.5 mg/day (with the exception of the 0.15–0.6 mg/day group in study #2, where the initial dose was 0.05 mg/day) and titrated to the target dosage range by approximately Day 7. Subsequently, dosage was increased to the maximum tolerated dose within the target dose range by Day 14. The primary efficacy variable in all studies was the mean change from baseline in total PANSS score.

Results of the studies demonstrated efficacy of RISPERDAL in all dose groups from 1–6 mg/day compared to placebo, as measured by significant reduction of total PANSS score. The efficacy on the primary parameter in the 1–3 mg/day group was comparable to the 4–6 mg/day group in study #1, and similar to the efficacy demonstrated in the 1.5–6 mg/day group in study #2. In study #2, the efficacy in the 1.5–6 mg/day group was statistically significantly greater than that in the 0.15–0.6 mg/day group. Doses higher than 3 mg/day did not reveal any trend towards greater efficacy.

14.2 Bipolar Mania - Monotherapy

Adults

The efficacy of RISPERDAL in the treatment of acute manic or mixed episodes was established in two short-term (3-week) placebo-controlled trials in patients who met the DSM-IV criteria for Bipolar I Disorder with manic or mixed episodes. These trials included patients with or without psychotic features.

The primary rating instrument used for assessing manic symptoms in these trials was the Young Mania Rating Scale (YMRS), an 11-item clinician-rated scale traditionally used to assess the degree of manic symptomatology (irritability, disruptive/aggressive behavior, sleep, elevated mood, speech, increased activity, sexual interest, language/thought disorder, thought content, appearance, and insight) in a range from 0 (no manic features) to 60 (maximum score). The primary outcome in these trials was change from baseline in the YMRS total score. The results of the trials follow:

- In one 3-week placebo-controlled trial (n=246), limited to patients with manic episodes, which involved a dose range of RISPERDAL 1–6 mg/day, once daily, starting at 3 mg/day (mean modal dose was 4.1 mg/day), RISPERDAL was superior to placebo in the reduction of YMRS total score.
- In another 3-week placebo-controlled trial (n=286), which involved a dose range of 1–6 mg/day, once daily, starting at 3 mg/day (mean modal dose was 5.6 mg/day), RISPERDAL was superior to placebo in the reduction of YMRS total score.

Pediatrics

The efficacy of RISPERDAL in the treatment of mania in children or adolescents with Bipolar I disorder was demonstrated in a 3-week, randomized, double-blind, placebo-controlled, multicenter trial including patients ranging in ages from 10 to 17 years who were experiencing a manic or mixed episode of bipolar I disorder. Patients were randomized into one of three treatment groups: RISPERDAL 0.5–2.5 mg/day (n=50, mean modal dose = 1.9 mg), RISPERDAL 3–6 mg/day (n=61, mean modal dose = 4.7 mg), or placebo (n=58). In all cases, study medication was initiated at 0.5 mg/day and titrated to the target dosage range by Day 7, with further increases in dosage to the maximum tolerated dose within the targeted dose range by Day 10. The primary rating instrument used for assessing efficacy in this study was the mean change from baseline in the total YMRS score.

Results of this study demonstrated efficacy of RISPERDAL in both dose groups compared with placebo, as measured by significant reduction of total YMRS score. The efficacy on the primary parameter in the 3–6 mg/day dose group was comparable to the 0.5–2.5 mg/day dose group. Doses higher than 2.5 mg/day did not reveal any trend towards greater efficacy.

14.3 Bipolar Mania – Adjunctive Therapy with Lithium or Valproate

The efficacy of RISPERDAL with concomitant lithium or valproate in the treatment of acute manic or mixed episodes was established in one controlled trial in adult patients who met the DSM-IV criteria for Bipolar I Disorder. This trial included patients with or without psychotic features and with or without a rapid-cycling course.

- In this 3-week placebo-controlled combination trial, 148 in- or outpatients on lithium or valproate therapy with inadequately controlled manic or mixed symptoms were randomized to receive RISPERDAL, placebo, or an active comparator, in combination with their original therapy. RISPERDAL, in a dose range of 1–6 mg/day, once daily, starting at 2 mg/day (mean modal dose of 3.8 mg/day), combined with lithium or valproate (in a therapeutic range of 0.6 mEq/L to 1.4 mEq/L or 50 mcg/mL to 120 mcg/mL, respectively) was superior to lithium or valproate alone in the reduction of YMRS total score.
- In a second 3-week placebo-controlled combination trial, 142 in- or outpatients on lithium, valproate, or carbamazepine therapy with inadequately controlled manic or mixed symptoms were randomized to receive RISPERDAL or placebo, in combination with their original therapy. RISPERDAL, in a dose range of 1–6 mg/day, once daily, starting at 2 mg/day (mean modal dose of 3.7 mg/day), combined with lithium, valproate, or carbamazepine (in therapeutic ranges of 0.6 mEq/L to 1.4 mEq/L for lithium, 50 mcg/mL to 125 mcg/mL for valproate, or 4–12 mcg/mL for carbamazepine, respectively) was not superior to lithium, valproate, or carbamazepine alone in the reduction of YMRS total score. A possible explanation for the failure of this trial was induction of risperidone and 9-hydroxyrisperidone clearance by carbamazepine, leading to subtherapeutic levels of risperidone and 9-hydroxyrisperidone.

14.4 Irritability Associated with Autistic Disorder

Short-Term Efficacy

The efficacy of RISPERDAL in the treatment of irritability associated with autistic disorder was established in two 8-week, placebo-controlled trials in children and adolescents (aged 5 to 16 years) who met the DSM-IV criteria for autistic disorder. Over 90% of these subjects were under 12 years of age and most weighed over 20 kg (16–104.3 kg).

Efficacy was evaluated using two assessment scales: the Aberrant Behavior Checklist (ABC) and the Clinical Global Impression - Change (CGI-C) scale. The primary outcome measure in both trials was the change from baseline to endpoint in the Irritability subscale of the ABC (ABC-I). The ABC-I subscale measured the emotional and behavioral symptoms of autism, including aggression towards others, deliberate self-injuriousness, temper tantrums, and quickly changing moods. The CGI-C rating at endpoint was a co-primary outcome measure in one of the studies.

The results of these trials are as follows:

- In one of the 8-week, placebo-controlled trials, children and adolescents with autistic disorder (n=101), aged 5 to 16 years, received twice daily doses of placebo or RISPERDAL 0.5–3.5 mg/day on a weight-adjusted basis. RISPERDAL, starting at 0.25 mg/day or 0.5 mg/day depending on baseline weight (< 20 kg and ≥ 20 kg, respectively) and titrated to clinical response (mean modal dose of 1.9 mg/day, equivalent to 0.06 mg/kg/day), significantly improved scores on the ABC-I subscale and on the CGI-C scale compared with placebo.
- In the other 8-week, placebo-controlled trial in children with autistic disorder (n=55), aged 5 to 12 years, RISPERDAL 0.02 to 0.06 mg/kg/day given once or twice daily, starting at 0.01 mg/kg/day and titrated to clinical response (mean modal dose of 0.05 mg/kg/day, equivalent to 1.4 mg/day), significantly improved scores on the ABC-I subscale compared with placebo.

A third trial was a 6-week, multicenter, randomized, double-blind, placebo-controlled, fixed-dose study to evaluate the efficacy and safety of a lower than recommended dose of risperidone in subjects (N=96) 5 to 17 years of age with autistic disorder (defined by DSM-IV criteria) and associated irritability and related behavioral symptoms. Approximately 77% of patients were younger than 12 years of age (mean age = 9), and 88% were male. Most patients (73%) weighed less than 45 kg (mean weight = 40 kg). Approximately 90% of patients were antipsychotic-naïve before entering the study.

There were two weight-based, fixed doses of risperidone (high-dose and low-dose). The high dose was 1.25 mg per day for patients weighing 20 to < 45 kg, and it was 1.75 mg per day for patients weighing ≥ 45 kg. The low dose was 0.125 mg per day for patients weighing 20 to < 45 kg, and it was 0.175 mg per day for patients weighing ≥ 45 kg. The dose was administered once daily in the morning, or in the evening if sedation occurred.

The primary efficacy endpoint was the mean change in the Aberrant Behavior Checklist – Irritability subscale (ABC-I) score from baseline to the end of Week 6. The study demonstrated the efficacy of high-dose risperidone, as measured by the mean change in ABC-I score. It did not demonstrate efficacy for low-dose risperidone. The mean baseline ABC-I scores were 29 in the placebo group (n=35), 27 in the risperidone low-dose group (n=30), and 28 in the risperidone high-dose group (n=31). The mean changes in ABC-I scores were -3.5, -7.4, and -12.4 in the placebo, low-dose, and high-dose group respectively. The results in the high-dose group were statistically significant (p< 0.001) but not in the low-dose group (p=0.164).

Long-Term Efficacy

Following completion of the first 8-week double-blind study, 63 patients entered an open-label study extension where they were treated with RISPERDAL for 4 or 6 months (depending on whether they received RISPERDAL or placebo in the double-blind study). During this open-label treatment period, patients were maintained on a mean modal dose of RISPERDAL of 1.8–2.1 mg/day (equivalent to 0.05 – 0.07 mg/kg/day).

Patients who maintained their positive response to RISPERDAL (response was defined as ≥ 25% improvement on the ABC-I subscale and a CGI-C rating of 'much improved' or 'very much improved') during the 4–6 month open-label treatment phase for about 140 days, on average, were randomized to receive RISPERDAL or placebo during an 8-week, double-blind withdrawal study (n=39 of the 63 patients). A pre-planned interim analysis of data from patients who completed the withdrawal study (n=32), undertaken by an independent Data Safety Monitoring Board, demonstrated a significantly lower relapse rate in the RISPERDAL group compared with the placebo group. Based on the interim analysis results, the study was terminated due to demonstration of a statistically significant effect on relapse prevention. Relapse was defined as ≥ 25% worsening on the most recent assessment of the ABC-I subscale (in relation to baseline of the randomized withdrawal phase).

16 HOW SUPPLIED/STORAGE AND HANDLING

16.1 How Supplied

RISPERDAL®(risperidone) Tablets

RISPERDAL®(risperidone) Tablets are imprinted"JANSSEN"on one side and either "Ris 0.5", "R1", "R2", "R3", or "R4" according to their respective strengths.

0.5 mg red-brown, capsule-shaped tablets: bottles of 60 NDC 50458-302-06, bottles of 500 NDC 50458-302-50, and hospital unit dose blister packs of 100 NDC 50458-302-01.

1 mg white, capsule-shaped tablets: bottles of 60 NDC 50458-300-06, bottles of 500 NDC 50458-300-50, and hospital unit dose blister packs of 100 NDC 50458-300-01.

2 mg orange, capsule-shaped tablets: bottles of 60 NDC 50458-320-06, bottles of 500 NDC 50458-320-50, and hospital unit dose blister packs of 100 NDC 50458-320-01.

3 mg yellow, capsule-shaped tablets: bottles of 60 NDC 50458-330-06, bottles of 500 NDC 50458-330-50, and hospital unit dose blister packs of 100 NDC 50458-330-01.

4 mg green, capsule-shaped tablets: bottles of 60 NDC 50458-350-06 and hospital unit dose blister packs of 100 NDC 50458-350-01.

RISPERDAL®(risperidone) Oral Solution

RISPERDAL®(risperidone) 1 mg/mL Oral Solution (NDC 50458-305-03) is supplied in 30 mL bottles with a calibrated (in milliliters) oral dosing syringe. The minimum calibrated volume is 0.25 mL, while the maximum calibrated volume is 3 mL.

RISPERDAL®M-TAB®(risperidone) Orally Disintegrating Tablets

RISPERDAL®M-TAB®(risperidone) Orally Disintegrating Tablets are etched on one side with "R0.5", "R1", "R2", "R3", or "R4" according to their respective strengths. RISPERDAL M-TAB Orally Disintegrating Tablets 0.5 mg, 1 mg, and 2 mg are packaged in blister packs of 4 (2 × 2) tablets. Orally Disintegrating Tablets 3 mg and 4 mg are packaged in a child-resistant pouch containing a blister with 1 tablet.

0.5 mg light coral, round, biconvex tablets: 7 blister packages (4 tablets each) per box, NDC 50458-395-28, and long-term care blister packaging of 30 tablets NDC 50458-395-30.

1 mg light coral, square, biconvex tablets: 7 blister packages (4 tablets each) per box, NDC 50458-315-28, and long-term care blister packaging of 30 tablets NDC 50458-315-30.

2 mg coral, square, biconvex tablets: 7 blister packages (4 tablets each) per box, NDC 50458-325-28.

3 mg coral, round, biconvex tablets: 28 blisters per box, NDC 50458-335-28.

4 mg coral, round, biconvex tablets: 28 blisters per box, NDC 50458-355-28.

16.2 Storage and Handling

RISPERDAL Tablets should be stored at controlled room temperature 15 °C to 25 °C (59 °F to 77 °F). Protect from light and moisture.

RISPERDAL 1 mg/mL Oral Solution should be stored at controlled room temperature 15 °C to 25 °C (59 °F to 77 °F). Protect from light and freezing.

RISPERDAL M-TAB Orally Disintegrating Tablets should be stored at controlled room temperature 15 °C to 25 °C (59 °F to 77 °F).

Keep out of reach of children.

17 PATIENT COUNSELING INFORMATION

Advise patients using RISPERDAL oral solution to read the FDA-approved patient labeling (Instructions for Use) for RISPERDAL oral solution.

Physicians are advised to discuss the following issues with patients for whom they prescribe RISPERDAL.

Neuroleptic Malignant Syndrome (NMS)

Counsel patients about a potentially fatal adverse reaction, Neuroleptic Malignant Syndrome (NMS), that has been reported in association with administration of antipsychotic drugs. Advise patients, family members, or caregivers to contact the healthcare provider or report to the emergency room if they experience signs and symptoms of NMS, including hyperpyrexia, muscle rigidity, altered mental status including delirium, and evidence of autonomic instability (irregular pulse or blood pressure, tachycardia, diaphoresis, and cardiac dysrhythmia) [see Warnings and Precautions (5.3)] .

Tardive Dyskinesia

Counsel patients on the signs and symptoms of tardive dyskinesia and to contact their healthcare provider if these abnormal movements occur [see Warnings and Precautions (5.4)] .

Metabolic Changes

Educate patients about the risk of metabolic changes, how to recognize symptoms of hyperglycemia and diabetes mellitus, and the need for specific monitoring, including blood glucose, lipids, and weight [see Warnings and Precautions (5.5)] .

Orthostatic Hypotension

Educate patients about the risk of orthostatic hypotension and syncope, particularly at the time of initiating treatment, re-initiating treatment, or increasing the dose [see Warnings and Precautions (5.7)] .

Leukopenia/Neutropenia

Advise patients with a pre-existing low WBC or a history of drug induced leukopenia/neutropenia they should have their CBC monitored while taking RISPERDAL [see Warnings and Precautions (5.9)] .

Hyperprolactinemia

Counsel patients on signs and symptoms of hyperprolactinemia that may be associated with chronic use of RISPERDAL. Advise them to seek medical attention if they experience any of the following: amenorrhea or galactorrhea in females, erectile dysfunction or gynecomastia in males. [see Warnings and Precautions (5.6)] .

Interference with Cognitive and Motor Performance

Caution patients about performing activities requiring mental alertness, such as operating hazardous machinery, or operating a motor vehicle until they are reasonably certain that RISPERDAL therapy does not affect them adversely [see Warnings and Precautions (5.10)] .

Priapism

Advise patients of the possibility of painful or prolonged penile erections (priapism). Instruct the patient to seek immediate medical attention in the event of priapism [see Warnings and Precautions (5.13)] .

Heat Exposure and Dehydration

Counsel patients regarding appropriate care in avoiding overheating and dehydration [see Warnings and Precautions (5.14)] .

Phenylketonurics

Inform patients with Phenylketonuria and caregivers that RISPERDAL M-TAB Orally Disintegrating Tablets contain phenylalanine. Phenylalanine is a component of aspartame. Each 4 mg RISPERDAL M-TAB Orally Disintegrating Tablet contains 0.84 mg phenylalanine; each 3 mg RISPERDAL M-TAB Orally Disintegrating Tablet contains 0.63 mg phenylalanine; each 2 mg RISPERDAL M-TAB Orally Disintegrating Tablet contains 0.42 mg phenylalanine; each 1 mg RISPERDAL M-TAB Orally Disintegrating Tablet contains 0.28 mg phenylalanine; and each 0.5 mg RISPERDAL M-TAB Orally Disintegrating Tablet contains 0.14 mg phenylalanine [see Warnings and Precautions (5.15)] .

Concomitant Medication

Advise patients to inform their healthcare providers if they are taking, or plan to take any prescription or over-the-counter drugs, as there is a potential for interactions [see Drug Interactions (7)] .

Alcohol

Advise patients to avoid alcohol while taking RISPERDAL [see Drug Interactions (7.2)] .

Pregnancy

Advise patients to notify their healthcare provider if they become pregnant or intend to become pregnant during treatment with RISPERDAL. Advise patients that RISPERDAL may cause extrapyramidal and/or withdrawal symptoms in a neonate. Advise patients that there is a pregnancy registry that monitors pregnancy outcomes in women exposed to RISPERDAL during pregnancy [see Use in Specific Populations (8.1)] .

Lactation

Advise breastfeeding women using RISPERDAL to monitor infants for somnolence, failure to thrive, jitteriness, and extrapyramidal symptoms (tremors and abnormal muscle movements) and to seek medical care if they notice these signs [see Use in Specific Populations (8.2)] .

Infertility

Advise females of reproductive potential that RISPERDAL may impair fertility due to an increase in serum prolactin levels. The effects on fertility are reversible [see Use in Specific Populations (8.3)].

RISPERDAL Tablets, RISPERDAL M-TAB Orally Disintegrating Tablets, and RISPERDAL Oral Solution are manufactured for:
Janssen Pharmaceuticals, Inc.
Titusville, NJ 08560, USA

For patent information: www.janssenpatents.com

© Johnson & Johnson and its affiliates 2007

INSTRUCTIONS FOR USE

RISPERDAL® (RISS-per-dal)
(risperidone)
Oral Solution

Read these Instructions for Use before you start using RISPERDAL Oral Solution and each time you get a refill. There may be new information. This information does not take the place of talking to your healthcare provider about your medical condition or treatment.

Important information you need to know before taking RISPERDAL Oral Solution:

- Take RISPERDAL Oral Solution exactly as your healthcare provider tells you to take it.
- Each 1 mL contains 1 mg of RISPERDAL Oral Solution.
- Ask your healthcare provider or pharmacist to show you how to measure your prescribed dose using the oral dosing syringe.
- Always use the oral dosing syringe that comes with RISPERDAL Oral Solution. Contact your healthcare provider or pharmacist if you lose or damage the oral dosing syringe, or if your carton does not come with one.
- RISPERDAL Oral Solution can be taken directly from the oral dosing syringe or mixed with water, coffee, orange juice, or low-fat milk. Do not mix RISPERDAL Oral Solution with cola or tea.

Each RISPERDAL Oral Solution carton contains:

- 1 bottle of RISPERDAL Oral Solution
- 1 oral dosing syringe

Gather and check supplies:

- Gather the RISPERDAL Oral Solution bottle and oral dosing syringe.
- Check the expiration date on the bottle. Do not use the bottle of RISPERDAL Oral Solution if the expiration date has passed.
- Check your dose in mLs as prescribed by your healthcare provider. Find this mL marking on the plunger of the oral dosing syringe. If your dose is more than 3 mL, you will need to divide your dose. Follow the instructions given to you by your healthcare provider or pharmacist on how to divide your dose.

Preparing a dose of RISPERDAL Oral Solution:

Step 1. Place the RISPERDAL Oral Solution bottle on a flat surface. Push down on the cap while turning it to the left (counterclockwise) to open the bottle.

Step 2. Push the plunger of the oral dosing syringe all the way down.

Step 3. With the bottle in an upright position, fully insert the oral dosing syringe into the opening of the bottle.

Step 4. Withdraw the prescribed dose of RISPERDAL Oral Solution from the bottle. Hold down the barrel of the oral dosing syringe with one hand. With your other hand, slowly pull the plunger up until you reach the mL markings on the plunger for the prescribed dose.

Step 5. Remove the oral dosing syringe from the bottle by holding the outer barrel and pulling straight up. Be careful not to push down on the plunger during this step.
Check the oral dosing syringe for air bubbles. If you see air bubbles, slowly push the plunger all the way down to return the oral solution into the bottle. Then repeat Step 4 to withdraw the prescribed dose.

Step 6. RISPERDAL Oral Solution can be mixed with a drink or taken directly from the oral dosing syringe.

- Mix the dose of RISPERDAL Oral Solution with water, coffee, orange juice, or low-fat milk. Stir well and drink all of the mixture right away to ensure the full dose is taken. See Figure 6a.
  Do not mix RISPERDAL Oral Solution with cola or tea.

Or

- To take the RISPERDAL Oral Solution dose directly from the oral dosing syringe, place the tip of the oral dosing syringe into the mouth and toward the cheek. Slowly push the plunger all the way down to gently release all of the medicine in the oral dosing syringe. Do not squirt or forcefully push the medicine into the back of the throat. See Figure 6b.

Step 7. Place the cap back on the RISPERDAL Oral Solution bottle and turn the cap to the right (clockwise) to close the bottle.

Step 8. Rinse the oral dosing syringe with water after each use.

- Remove the plunger from the oral dosing syringe barrel.
- Rinse the oral dosing syringe barrel and plunger with water and let them air dry.
- When the oral dosing syringe barrel and plunger are dry, put the plunger back into the oral dosing syringe barrel for the next use.

Do not throw away the oral dosing syringe.

Storing RISPERDAL Oral Solution:

- Store RISPERDAL Oral Solution at room temperature between 59 °F to 77 °F (15 °C to 25 °C).
- Do not freeze RISPERDAL Oral Solution. Protect from light.
- Keep RISPERDAL Oral Solution and all medicines out of the reach of children.

Manufactured for:
Janssen Pharmaceuticals, Inc.
Titusville, NJ, 08560, USA

For patent information: www.jansenpatents.com

© Johnson & Johnson and its affiliates 2007

This Instructions for Use has been approved by the U.S. Food and Drug Administration.
Issued: 2/2025

INSTRUCCIONES DE USO

RISPERDAL®(RISS-per-dal)
(risperidona)
Solución oral

Lea estas Instrucciones de uso antes de comenzar a usar RISPERDAL Solución oral y cada vez que renueve su receta. Es posible que este material contenga información nueva. Esta información no reemplaza la consulta con su proveedor de atención médica acerca de su enfermedad o tratamiento.

Información importante que debe saber antes de tomar RISPERDAL Solución oral:

- Tome RISPERDAL Solución oral exactamente como se lo indica su proveedor de atención médica.
- Cada 1 ml contiene 1 mg de RISPERDAL Solución oral.
- Pídale a su proveedor de atención médica o farmacéutico que le muestre cómo medir la dosis recetada con la jeringa de dosificación oral.
- Utilice siempre la jeringa de dosificación oral que viene con RISPERDAL Solución oral. Comuníquese con su proveedor de atención médica o farmacéutico si pierde o daña la jeringa de dosificación oral, o si su caja no viene con una.
- RISPERDAL Solución oral se puede tomar directamente de la jeringa de dosificación oral o se puede mezclar con agua, café, jugo de naranja o leche con bajo contenido de grasa. Nomezcle RISPERDAL Solución oral con refrescos de cola o té.

Cada caja de RISPERDAL Solución oral contiene lo siguiente:

- 1 frasco de RISPERDAL Solución oral
- 1 jeringa de dosificación oral

Reúna y verifique los suministros:

- Reúna el frasco de RISPERDAL Solución oral y la jeringa de dosificación oral.
- Consulte la fecha de caducidad en el frasco. No utilice el frasco de RISPERDAL Solución oral si ha pasado la fecha de caducidad.
- Verifique su dosis en ml según lo prescrito por su proveedor de atención médica. Busque esta marca de ml en el émbolo de la jeringa de dosificación oral. Si su dosis supera los 3 ml, deberá dividir la dosis. Siga las instrucciones que le dé su proveedor de atención médica o farmacéutico sobre cómo dividir su dosis.

Preparación de una dosis de RISPERDAL Solución oral:

Paso 1.Coloque el frasco de RISPERDAL Solución oral sobre una superficie plana. Empuje hacia abajo la tapa mientras la gira hacia la izquierda (en sentido antihorario) para abrir el frasco.

Paso 2.Empuje el émbolo de la jeringa de dosificación oral hasta el fondo.

Paso 3.Con el frasco en posición vertical, inserte completamente la jeringa de dosificación oral en la abertura del frasco.

Paso 4.Extraiga la dosis prescrita de RISPERDAL Solución oral del frasco. Sostenga el cilindro de la jeringa de dosificación oral con una mano. Con la otra mano, tire lentamente del émbolo hacia arriba hasta que alcance las marcas de ml en el émbolo para la dosis prescrita.

Paso 5.Retire la jeringa de dosificación oral del frasco sujetando el cilindro exterior y tirando hacia arriba. Tenga cuidado de no empujar hacia abajo el émbolo durante este paso.
Compruebe que no haya burbujas de aire en la jeringa de dosificación oral. Si ve burbujas de aire, empuje lentamente el émbolo hasta el fondo para devolver la solución oral al frasco. Luego repita el Paso 4para retirar la dosis prescrita.

Paso 6.RISPERDAL Solución oral se puede mezclar con una bebida o se puede tomar directamente de la jeringa de dosificación oral.

- Mezcle la dosis de RISPERDAL Solución oral con agua, café, jugo de naranja o leche con bajo contenido de grasa. Revuelva bien y beba toda la mezcla de inmediato para asegurarse de tomar la dosis completa. Consulte la Figura 6a.
  No mezcleRISPERDAL Solución oral con refrescos de cola o té.

O

- Para tomar la dosis de RISPERDAL Solución oral directamente de la jeringa de dosificación oral, coloque la punta de la jeringa de dosificación oral en la boca y hacia la mejilla. Empuje lentamente el émbolo hasta el fondo para liberar suavemente todo el medicamento en la jeringa de dosificación oral. No rocíe ni empuje con fuerza el medicamento en la parte posterior de la garganta. Consulte la Figura 6b.

Paso 7.Vuelva a colocar la tapa en el frasco de RISPERDAL Solución oral y gírela hacia la derecha (en el sentido de las agujas del reloj) para cerrar el frasco.

Paso 8.Enjuague la jeringa de dosificación oral con agua después de cada uso.

- Retire el émbolo del cilindro de la jeringa de dosificación oral.
- Enjuague el cilindro de la jeringa de dosificación oral con agua y déjela secar al aire.
- Cuando el cilindro de la jeringa de dosificación oral y el émbolo estén secos, vuelva a colocar el émbolo en el cilindro de la jeringa de dosificación oral para el próximo uso.

No deseche la jeringa de dosificación oral.

Almacenamiento de RISPERDAL Solución oral

- Almacene RISPERDAL Solución oral a temperatura ambiente entre 59 °F y 77 °F (de 15 °C a 25 °C).
- No congelar RISPERDAL Solución oral. Proteger de la luz.
- Mantenga RISPERDAL Solución oral y todos los medicamentos fuera del alcance de los niños.

Fabricado para:

Janssen Pharmaceuticals, Inc.

Titusville, NJ, 08560, USA

Estas Instrucciones de uso han sido aprobadas por la Administración de Alimentos y Medicamentos (FDA) de los EE. UU.

Para información sobre patentes : www.janssenpatents.com

© Johnson & Johnson y sus afiliados 2007

Revisado: 2/2025

PRINCIPAL DISPLAY PANEL - 0.5 mg Bottle Label

NDC50458-302-06

RISPERDAL®
(risperiDONE)
TABLETS

0.5 mg

Each tablet contains:Risperidone 0.5 mg

Keep out of reach of children.

Rx only

60 Tablets

PRINCIPAL DISPLAY PANEL - 1 mg Bottle Label

NDC50458-300-06

RISPERDAL®
(risperiDONE)
TABLETS

1 mg

Each tablet contains:Risperidone 1 mg

Keep out of reach of children.

Rx only

60 Tablets

PRINCIPAL DISPLAY PANEL - 2 mg Bottle Label

NDC50458-320-06

RISPERDAL®
(risperiDONE)
TABLETS

2 mg

Each tablet contains:Risperidone 2 mg

Keep out of reach of children.

Rx only

60 Tablets

PRINCIPAL DISPLAY PANEL - 3 mg Bottle Label

60 TABLETS
NDC 50458-330-06

RISPERDAL®
(risperiDONE)
TABLETS

3 mg

Each tablet contains:Risperidone 3 mg

Keep out of reach of children.

Rx only

60 Tablets

PRINCIPAL DISPLAY PANEL - 4 mg Bottle Label

60 TABLETS
NDC 50458-350-06

RISPERDAL®
(risperiDONE)
TABLETS

4 mg

Each tablet contains:Risperidone 4 mg

Keep out of reach of children.

Rx only

60 Tablets

PACKAGE LABEL

PRINCIPAL DISPLAY PANEL - 0.5 mg Tablet Carton

NDC 50458-395-28
28 TABLETS

Risperdal® M-TAB®
risperiDONE Orally Disintegrating Tablets

0.5 mg

Rx Only
Each tablet contains:
0.5 mg risperidone

Blister pack
7 cards of 4 tablets

janssen

PACKAGE LABEL

PRINCIPAL DISPLAY PANEL - 1 mg Tablet Carton

NDC 50458-315-28
28 TABLETS

Risperdal® M-TAB®
risperiDONE Orally Disintegrating Tablets

1 mg

Rx Only
Each tablet contains:
1 mg risperidone

Blister pack
7 cards of 4 tablets

janssen

PACKAGE LABEL

PRINCIPAL DISPLAY PANEL - 2 mg Tablet Carton

NDC 50458-325-28
28 TABLETS

Risperdal® M-TAB®
risperiDONE Orally Disintegrating Tablets

2 mg

Rx Only
Each tablet contains:
2 mg risperidone

Blister pack
7 cards of 4 tablets

janssen

PACKAGE LABEL

PRINCIPAL DISPLAY PANEL - 3 mg Tablet Carton

NDC 50458-335-28

Risperdal® M-TAB®
risperiDONE Orally Disintegrating Tablets

Phenylketonurics:Contains 0.63 mg phenylalanine (a component of aspartame) per 3 mg tablet
Each tablet contains:3 mg risperidone

Rx only

Dosage:For information or use, see accompanying full Prescribing Information.

Product of Ireland

Manufactured by:
Janssen Ortho, LLC
Gurabo, PR 00778

Manufactured for:
Janssen Pharmaceuticals, Inc.
Titusville, NJ 08560

janssen

PACKAGE LABEL

PRINCIPAL DISPLAY PANEL - 4 mg Tablet Carton

NDC 50458-355-28

Risperdal® M-TAB®
risperiDONE Orally Disintegrating Tablets

Phenylketonurics:Contains 0.84 mg phenylalanine (a component of aspartame) per 4 mg tablet
Each tablet contains:4 mg risperidone

Rx only

Dosage:For information or use, see accompanying full Prescribing Information.

Product of Ireland

Manufactured by:
Janssen Ortho, LLC
Gurabo, PR 00778

Manufactured for:
Janssen Pharmaceuticals, Inc.
Titusville, NJ 08560

janssen

PACKAGE LABEL

PRINCIPAL DISPLAY PANEL - 30 mL Bottle Carton

NDC50458-305-03
RISPERDAL®

(risperiDONE)
ORAL SOLUTION

1 mg/mL

Each 1 mL contains 1 mg of risperidone in an aqueous solution.

Rx only

30 mL

Johnson&Johnson